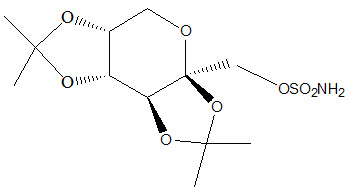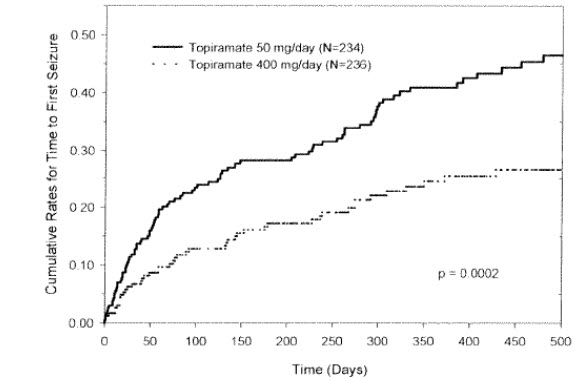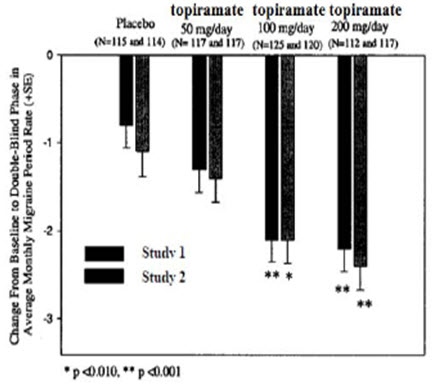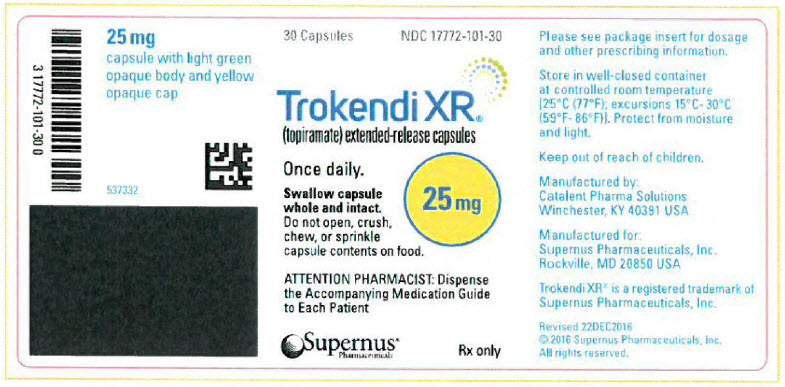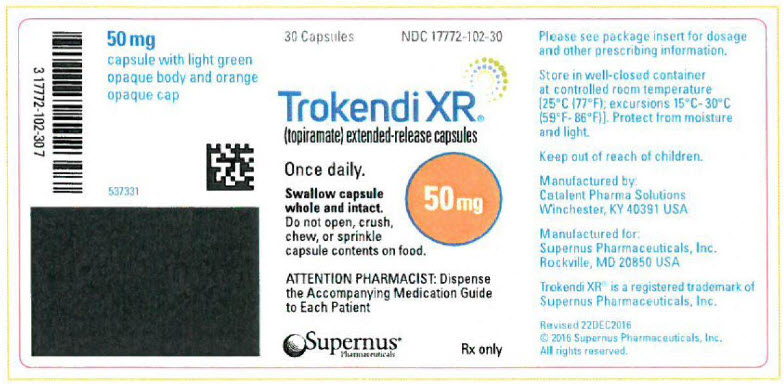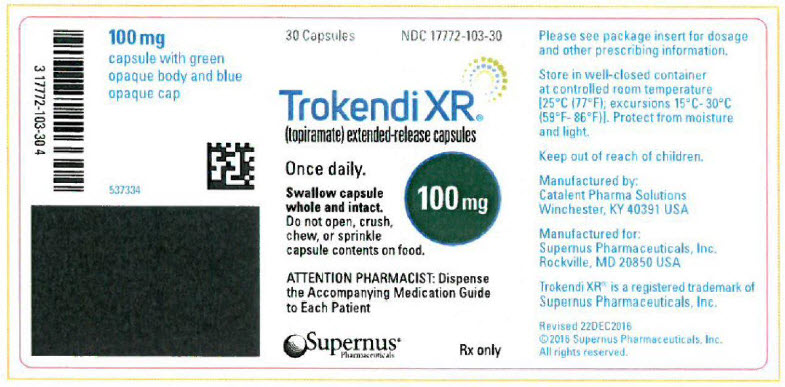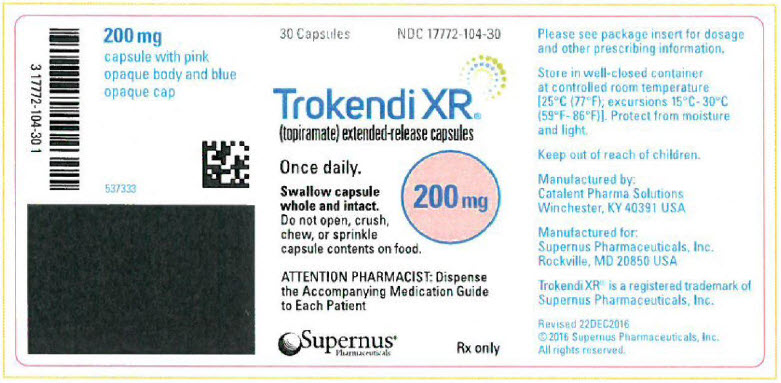 DRUG LABEL: Trokendi XR
NDC: 17772-102 | Form: CAPSULE, EXTENDED RELEASE
Manufacturer: Supernus Pharmaceuticals
Category: prescription | Type: HUMAN PRESCRIPTION DRUG LABEL
Date: 20251022

ACTIVE INGREDIENTS: TOPIRAMATE 50 mg/1 1
INACTIVE INGREDIENTS: POLYVINYL ALCOHOL, UNSPECIFIED; TITANIUM DIOXIDE; TALC; XANTHAN GUM; GELATIN, UNSPECIFIED; FD&C BLUE NO. 1; FERRIC OXIDE YELLOW; FD&C RED NO. 3; FD&C YELLOW NO. 6; GLYCERIN; SOYBEAN LECITHIN; SHELLAC; HYPROMELLOSE 2910 (5 MPA.S); FERROSOFERRIC OXIDE; MANNITOL; DOCUSATE SODIUM/SODIUM BENZOATE; ETHYLCELLULOSE, UNSPECIFIED; OLEIC ACID; MEDIUM-CHAIN TRIGLYCERIDES; POLYETHYLENE GLYCOL, UNSPECIFIED

HIGHLIGHTS OF PRESCRIBING INFORMATION

These highlights do not include all the information needed to use TROKENDI XR® safely and effectively. See full prescribing information for TROKENDI XR®.
TROKENDI XR® (topiramate) extended-release capsules, for oral use
Initial U.S. Approval: 1996

1 INDICATIONS AND USAGE

TROKENDI XR®is indicated for:

- Epilepsy: initial monotherapy for the treatment of partial-onset or primary generalized tonic-clonic seizures in patients 6 years of age and older (1.1); adjunctive therapy for the treatment of partial-onset, primary generalized tonic-clonic seizures, or seizures associated with Lennox-Gastaut syndrome (LGS) in patients 6 years of age and older (1.2)
- Preventive treatment of migraine in patients 12 years of age and older (1.3)

2 DOSAGE AND ADMINISTRATION

- TROKENDI XR®initial dose, titration, and recommended maintenance dose varies by indication and age group. See Full Prescribing Information for recommended dosage, and dosing considerations in patients with renal impairment, geriatric patients, and patients undergoing hemodialysis (2.1, 2.2, 2.3, 2.4, 2.5, 2.6)
- Swallow capsule whole and intact. Do not sprinkle on food, chew, or crush (2.7)

3 DOSAGE FORMS AND STRENGTHS

Extended-release capsules: 25 mg, 50 mg, 100 mg, and 200 mg (3)

4 CONTRAINDICATIONS

- With recent alcohol use, i.e., within 6 hours prior to and 6 hours after TROKENDI XR®use (4, 5.5)

5 WARNINGS AND PRECAUTIONS

- Acute myopia and secondary angle closure glaucoma: can lead to permanent visual loss; discontinue TROKENDI XR®as soon as possible (5.1)
- Visual field defects: consider discontinuation of TROKENDI XR (5.2)
- Oligohydrosis and hyperthermia: monitor decreased sweating and increased body temperature, especially in pediatric patients (5.3)
- Metabolic acidosis: baseline and periodic measurement of serum bicarbonate is recommended; consider dose reduction or discontinuation of TROKENDI XR®if clinically appropriate (5.4)
- Suicidal behavior and ideation: antiepileptic drugs increase the risk of suicidal behavior or ideation (5.6)
- Cognitive/neuropsychiatric adverse reactions: use caution when operating machinery including cars; depression and mood problems may occur (5.7)
- Fetal toxicity: use during pregnancy can cause major congenital malformations, including but not limited to cleft lip and/or palate, and being small for gestational age (5.8)
- Withdrawal of AEDs: withdraw TROKENDI XR®gradually (5.9)
- Decrease in Bone Mineral Density: has been shown to decrease bone mineral density and bone mineral content in pediatric patients (5.10)
- Negative effects on growth (height and weight): may slow height increase and weight gain; carefully monitor children receiving prolonged therapy (5.11)
- Serious skin reactions: If SJS or TEN is suspected, discontinue TROKENDI XR (5.12)
- Hyperammonemia/encephalopathy: measure ammonia if encephalopathic symptoms occur (5.13)
- Kidney stones: avoid use with other carbonic anhydrase inhibitors, other drugs causing metabolic acidosis, or in patients on a ketogenic diet (5.14)
- Hypothermia has been reported with and without hyperammonemia during topiramate treatment with concomitant valproic acid use (5.15)

6 ADVERSE REACTIONS

Epilepsy:Most common (≥ 10% more frequent than placebo or low-dose topiramate) adverse reactions in adult and pediatric patients were paresthesia, anorexia, weight loss, speech disorders/related speech problems, fatigue, dizziness, somnolence, nervousness, psychomotor slowing, abnormal vision, and fever (6.1).

Migraine:Most common (≥5% more frequent than placebo) adverse reactions in adult and pediatric patients were: paresthesia, anorexia, weight loss, difficulty with memory, taste perversion, diarrhea, hypoesthesia, nausea, abdominal pain, and upper respiratory tract infection (6.1).

To report SUSPECTED ADVERSE REACTIONS, contact Supernus Pharmaceuticals at 1-866-398-0833 or the FDA at 1-800-FDA-1088 or www.fda.gov/medwatch.

7 DRUG INTERACTIONS

- Contraceptives: Decreased contraceptive efficacy and increased breakthrough bleeding, especially at doses greater than 200 mg per day (7.5)
- Monitor lithium levels if lithium is used with high-dose TROKENDI XR (7.8)

FULL PRESCRIBING INFORMATION

1 INDICATIONS AND USAGE

1.1 Monotherapy Epilepsy

TROKENDI XR®is indicated as initial monotherapy for the treatment of partial-onset or primary generalized tonic-clonic seizures in patients 6 years of age and older [see Clinical Studies (14.2)] .

1.2 Adjunctive Therapy Epilepsy

TROKENDI XR®is indicated as adjunctive therapy for the treatment of partial-onset seizures, primary generalized tonic-clonic seizures, and seizures associated with Lennox-Gastaut syndrome in patients 6 years of age and older [see Clinical Studies (14.3)] .

1.3 Migraine

TROKENDI XR®is indicated for the preventive treatment of migraine in patients 12 years of age and older [see Clinical Studies (14.4)] .

2 DOSAGE AND ADMINISTRATION

2.1 Dosing in Monotherapy Epilepsy

Adults and Pediatric Patients 10 Years of Age and Older with Partial Onset or Primary Generalized Tonic-Clonic Seizures

The recommended dose for TROKENDI XR monotherapy in adults and in pediatric patients 10 years of age and older is 400 mg orally once daily. Titrate TROKENDI XR®according to the following schedule:

 | Week 1: | 50 mg once daily
 | Week 2: | 100 mg once daily
 | Week 3: | 150 mg once daily
 | Week 4: | 200 mg once daily
 | Week 5: | 300 mg once daily
 | Week 6: | 400 mg once daily

Pediatric Patients Ages 6 to 9 Years of Age

Dosing in patients 6 to 9 years of age is based on weight. During the titration period, the initial dose of TROKENDI XR®is 25 mg/day nightly for the first week. Based upon tolerability, the dosage can be increased to 50 mg/day in the second week. Dosage can be increased by 25 mg to 50 mg/day each subsequent week as tolerated. Titration to the minimum maintenance dose should be attempted over 5-7 weeks of the total titration period. Based upon tolerability and clinical response, additional titration to a higher dose (up to the maximum maintenance dose) can be attempted at 25 mg to 50 mg/day weekly increments. The total daily dose should not exceed the maximum maintenance dose for each range of body weight (see Table 1).

Table 1: Monotherapy Target Total Daily Maintenance Dosing for Patients 6 to 9 Years of Age
Weight (kg) | Total Daily Dose (mg/day) Minimum Maintenance Dose | Total Daily Dose (mg/day) Maximum Maintenance Dose
Up to 11 | 150 | 250
12 - 22 | 200 | 300
23 - 31 | 200 | 350
32 - 38 | 250 | 350
Greater than 38 | 250 | 400

2.2 Dosing in Adjunctive Therapy Epilepsy

Adults (17 Years of Age and Older)

The recommended total daily dose of TROKENDI XR®as adjunctive therapy in adults with partial-onset seizures or Lennox-Gastaut Syndrome is 200 mg to 400 mg orally once daily and with primary generalized tonic-clonic seizures is 400 mg orally once daily. Initiate therapy at 25 mg to 50 mg once daily followed by titration to an effective dose in increments of 25 mg to 50 mg every week. Titrating in increments of 25 mg/day every week may delay the time to reach an effective dose. Doses above 400 mg/day have not been shown to improve responses in adults with partial-onset seizures.

Pediatric Patients 6 to 16 Years of Age

The recommended total daily dose of TROKENDI XR®as adjunctive therapy for patients 6 to 16 years of age with partial-onset seizures, primary generalized tonic-clonic seizures, or seizures associated with Lennox-Gastaut syndrome is approximately 5 mg/kg to 9 mg/kg orally once daily. Begin titration at 25 mg once daily (or less, based on a range of 1 mg/kg/day to 3 mg/kg/day) given nightly for the first week. Subsequently, increase the dosage at 1- or 2-week intervals by increments of 1 mg/kg/day to 3 mg/kg/day to achieve optimal clinical response. Dose titration should be guided by clinical outcome. The total daily dose should not exceed 400 mg/day.

2.3 Dosing for the Preventive Treatment of Migraine

The recommended total daily dose of TROKENDI XR®as treatment for the preventive treatment of migraine in patients 12 years of age and older is 100 mg once daily. Titrate TROKENDI XR®for the preventive treatment of migraine according to the following schedule:

 | Week 1: | 25mg once daily
 | Week 2: | 50mg once daily
 | Week 3: | 75mg once daily
 | Week 4: | 100mg once daily

Dose and titration rate should be guided by clinical outcome. If required, longer intervals between dose adjustments can be used.

2.4 Administration With Alcohol

Alcohol use should be completely avoided within 6 hours prior to and 6 hours after TROKENDI XR®administration [see Warnings and Precautions (5.5)] .

2.5 Dose Modifications in Patients With Renal Impairment

In patients with renal impairment (creatinine clearance less than 70 mL/min/1.73 m^2), one-half of the usual adult dose of TROKENDI XR is recommended [see Use in Specific Populations (8.5, 8.6), Clinical Pharmacology (12.3)] .

2.6 Dosage Modifications in Patients Undergoing Hemodialysis

To avoid rapid drops in topiramate plasma concentration during hemodialysis, a supplemental dose of TROKENDI XR may be required. The actual adjustment should take into account 1) the duration of dialysis period, 2) the clearance rate of the dialysis system being used, and 3) the effective renal clearance of topiramate in the patient being dialyzed [see Use in Specific Populations (8.7), Clinical Pharmacology (12.3)] .

2.7 Administration Instructions

TROKENDI XR®can be taken without regard to meals.

Swallow capsule whole and intact. Do not sprinkle on food, chew, or crush.

3 DOSAGE FORMS AND STRENGTHS

TROKENDI XR®extended-release capsules are available in the following strengths and colors:

- 25 mg: Size 2 capsules, light green opaque body/yellow opaque cap (printed "SPN" on the cap, "25" on the body)
- 50 mg: Size 0 capsules, light green opaque body/orange opaque cap (printed "SPN" on the cap, "50" on the body)
- 100 mg: Size 00 capsules, green opaque body/blue opaque cap (printed "SPN" on the cap, "100" on the body)
- 200 mg: Size 00 capsules, pink opaque body/blue opaque cap (printed "SPN" on the cap, "200" on the body)

4 CONTRAINDICATIONS

TROKENDI XR®is contraindicated in patients with recent alcohol use (i.e., within 6 hours prior to and 6 hours after TROKENDI XR®use) [see Warnings and Precautions (5.5)]

5 WARNINGS AND PRECAUTIONS

5.1 Acute Myopia and Secondary Angle Closure Glaucoma Syndrome

A syndrome consisting of acute myopia associated with secondary angle closure glaucoma has been reported in patients receiving topiramate. Symptoms include acute onset of decreased visual acuity and/or ocular pain. Ophthalmologic findings can include some or all of the following: myopia, mydriasis, anterior chamber shallowing, ocular hyperemia (redness), choroidal detachments, retinal pigment epithelial detachments, macular striae, and increased intraocular pressure. This syndrome may be associated with supraciliary effusion resulting in anterior displacement of the lens and iris, with secondary angle closure glaucoma. Symptoms typically occur within 1 month of initiating topiramate therapy. In contrast to primary narrow angle glaucoma, which is rare under 40 years of age, secondary angle closure glaucoma associated with topiramate has been reported in pediatric patients as well as adults. The primary treatment to reverse symptoms is discontinuation of TROKENDI XR®as rapidly as possible, according to the judgment of the treating physician. Other measures, in conjunction with discontinuation of TROKENDI XR®, may be helpful.

Elevated intraocular pressure of any etiology, if left untreated, can lead to serious sequelae including permanent vision loss.

5.2 Visual Field Defects

Visual field defects (independent of elevated intraocular pressure) have been reported in clinical trials and in postmarketing experience in patients receiving topiramate. In clinical trials, most of these events were reversible after topiramate discontinuation. If visual problems occur at any time during treatment with TROKENDI XR, consideration should be given to discontinuing the drug.

5.3 Oligohydrosis and Hyperthermia

Oligohydrosis (decreased sweating), resulting in hospitalization in some cases, has been reported in association with topiramate use. Decreased sweating and an elevation in body temperature above normal characterized these cases. Some of the cases were reported after exposure to elevated environmental temperatures.

The majority of the reports have been in pediatric patients. Patients, especially pediatric patients, treated with TROKENDI XR®should be monitored closely for evidence of decreased sweating and increased body temperature, especially in hot weather. Caution should be used when TROKENDI XR®is given with other drugs that predispose patients to heat-related disorders; these drugs include, but are not limited to, other carbonic anhydrase inhibitors and drugs with anticholinergic activity .

5.4 Metabolic Acidosis

TROKENDI XR®can cause hyperchloremic, non-anion gap, metabolic acidosis (i.e., decreased serum bicarbonate below the normal reference range in the absence of chronic respiratory alkalosis). This metabolic acidosis is caused by renal bicarbonate loss due carbonic anhydrase inhibition by TROKENDI XR. TROKENDI XR®-induced metabolic acidosis can occur at any time during treatment. Bicarbonate decrements are usually mild to moderate (average decrease of 4 mEq/L at daily doses of 400 mg in adults and at approximately 6 mg/kg/day in pediatric patients); rarely, patients can experience severe decrements to values below 10 mEq/L. Conditions or therapies that predispose patients to acidosis (such as renal disease, severe respiratory disorders, status epilepticus, diarrhea, ketogenic diet, or specific drugs) may be additive to the bicarbonate lowering effects of TROKENDI XR.

Metabolic acidosis was commonly observed in adult and pediatric patients treated with immediate-release topiramate in clinical trials. The incidence of decreased serum bicarbonate in pediatric trials for adjunctive treatment of Lennox-Gastaut syndrome or refractory partial onset seizures was as high as 67% for immediate-release topiramate (at approximately 6 mg/kg/day), and 10% for placebo. The incidence of a markedly abnormally low serum bicarbonate (i.e., absolute value <17 mEq/L and ≥ 5 mEq/L decrease from pretreatment) in these trials was up to 11%, compared to ≤ 2% for placebo.

Manifestations of acute or chronic metabolic acidosis may include hyperventilation, nonspecific symptoms such as fatigue and anorexia, or more severe sequelae including cardiac arrhythmias or stupor. Chronic, untreated metabolic acidosis may increase the risk for nephrolithiasis or nephrocalcinosis and may also result in osteomalacia (referred to as rickets in pediatric patients) and/or osteoporosis with an increased risk for fractures [see Warnings and Precautions (5.10, 5.14)] . A one-year, active-controlled study of pediatric patients treated with immediate-release topiramate demonstrated that immediate-release topiramate decreased lumbar spine bone mineral density and that this lumbar spine bone mineral density decrease was correlated (using change from baseline for lumbar spine Z score at final visit versus lowest post-treatment serum bicarbonate) with decreased serum bicarbonate, a reflection of metabolic acidosis [see Warnings and Precautions (5.10), Use in Specific Populations (8.4)]. Chronic metabolic acidosis in pediatric patients may also reduce growth rates, which may decrease the maximal height achieved. Long-term, open-label treatment of pediatric patients 1 to 24 months old with intractable partial epilepsy, for up to 1 year, showed reductions from baseline in length, weight, and head circumference compared to age and sex-matched normative data, although these patients with epilepsy are likely to have different growth rates than normal 1 to 24 month old pediatrics. Reductions in length and weight were correlated to the degree of acidosis [see Use in Specific Populations (8.4)] . TROKENDI XR treatment that causes metabolic acidosis during pregnancy can possibly produce adverse effects on the fetus and might also cause metabolic acidosis in the neonate from possible transfer of topiramate to the fetus [see Warnings and Precautions (5.8)and Use in Specific Populations (8.1)] .

Measurement of Serum Bicarbonate in Epilepsy and Migraine Patients

Measurement of baseline and periodic serum bicarbonate during topiramate treatment is recommended. If metabolic acidosis develops and persists, consideration should be given to reducing the dose or discontinuing TROKENDI XR (using dose tapering). If the decision is made to continue patients on TROKENDI XR in the face of persistent acidosis, alkali treatment should be considered.

5.5 Interaction With Alcohol

In vitrodata show that, in the presence of alcohol, the pattern of topiramate release from TROKENDI XR®capsules is significantly altered. As a result, plasma levels of topiramate with TROKENDI XR®may be markedly higher soon after dosing and subtherapeutic later in the day. Therefore, alcohol use should be completely avoided within 6 hours prior to and 6 hours after TROKENDI XR®administration .

5.6 Suicidal Behavior and Ideation

Antiepileptic drugs (AEDs) increase the risk of suicidal thoughts or behavior in patients taking these drugs for any indication. Patients treated with any AED, including TROKENDI XR®for any indication should be monitored for the emergence or worsening of depression, suicidal thoughts, or behavior, and/or any unusual changes in mood or behavior.

Pooled analyses of 199 placebo-controlled clinical trials (mono- and adjunctive therapy) of 11 different AEDs showed that patients randomized to one of the AEDs had approximately twice the risk (adjusted Relative Risk 1.8, 95% CI:1.2, 2.7) of suicidal thinking or behavior compared to patients randomized to placebo. In these trials, which had a median treatment duration of 12 weeks, the estimated incidence rate of suicidal behavior or ideation among 27,863 AED-treated patients was 0.43%, compared to 0.24% among 16,029 placebo-treated patients, representing an increase of approximately one case of suicidal thinking or behavior for every 530 patients treated. There were four suicides in drug-treated patients in the trials and none in placebo-treated patients, but the number is too small to allow any conclusion about drug effect on suicide.

The increased risk of suicidal thoughts or behavior with AEDs was observed as early as one week after starting drug treatment with AEDs and persisted for the duration of treatment assessed. Because most trials included in the analysis did not extend beyond 24 weeks, the risk of suicidal thoughts or behavior beyond 24 weeks could not be assessed.

The risk of suicidal thoughts or behavior was generally consistent among drugs in the data analyzed. The finding of increased risk with AEDs of varying mechanisms of action and across a range of indications suggests that the risk applies to all AEDs used for any indication. The risk did not vary substantially by age (5 to 100 years) in the clinical trials analyzed.

Table 2 shows absolute and relative risk by indication for all evaluated AEDs.

Table 2: Risk by Indication for Antiepileptic Drugs in the Pooled Analysis
Indication | Placebo Patients with Events per 1,000 Patients | Drug Patients with Events per 1,000 Patients | Relative Risk: Incidence of Events in Drug Patients/Incidence in Placebo Patients | Risk Difference: Additional Drug Patients with Events per 1,000 Patients
Epilepsy | 1.0 | 3.4 | 3.5 | 2.4
Psychiatric | 5.7 | 8.5 | 1.5 | 2.9
Other | 1.0 | 1.8 | 1.9 | 0.9
Total | 2.4 | 4.3 | 1.8 | 1.9

The relative risk for suicidal thoughts or behavior was higher in clinical trials for epilepsy than in clinical trials for psychiatric or other conditions, but the absolute risk differences were similar for the epilepsy and psychiatric indications.

Anyone considering prescribing TROKENDI XR®or any other AED must balance the risk of suicidal thoughts or behavior with the risk of untreated illness. Epilepsy and many other illnesses for which AEDs are prescribed are themselves associated with morbidity and mortality and an increased risk of suicidal thoughts and behavior. Should suicidal thoughts and behavior emerge during treatment, the prescriber needs to consider whether the emergence of these symptoms in any given patient may be related to the illness being treated.

5.7 Cognitive/Neuropsychiatric Adverse Reactions

Immediate-release topiramate can cause, and therefore expected to be caused by TROKENDI XR®, cognitive/neuropsychiatric adverse reactions. The most frequent of these can be classified into three general categories: 1) Cognitive-related dysfunction (e.g., confusion, psychomotor slowing, difficulty with concentration/attention, difficulty with memory, speech or language problems, particularly word-finding difficulties); 2) Psychiatric/behavioral disturbances (e.g., depression or mood problems); and 3) Somnolence or fatigue.

Adult Patients

Cognitive-Related Dysfunction

Rapid titration rate and higher initial dose were associated with higher incidences of cognitive-related dysfunction.

In adult adjunctive epilepsy controlled trials, which used rapid titration (100-200 mg/day weekly increments), and target immediate-release topiramate doses of 200 mg – 1000 mg/day, 56% of patients in the 800 mg/day and 1000 mg/day dose groups experienced cognitive-related dysfunction compared to approximately 42% of patients in the 200 - 400 mg/day groups and 14% for placebo. In this rapid titration regimen, these dose-related adverse reactions began in the titration or in the maintenance phase, and in some patients these events began during titration and persisted into the maintenance phase.

In the monotherapy epilepsy controlled trial conducted with immediate-release topiramate, the proportion of patients who experienced one or more cognitive-related adverse reactions was 19% for topiramate 50 mg per day and 26% for 400 mg per day.

In the 6-month controlled trials for the preventive treatment of migraine with immediate release topiramate using a slower titration regimen (25mg per day weekly increments), the proportion of patients who experienced one or more cognitive-related adverse reactions was 19% for topiramate 50 mg per day, 22% for 100 mg per day (the recommended dose), 28% for 200 mg per day and 10% for placebo. Cognitive adverse reactions most commonly developed during titration and sometimes persisted after completion of titration.

Psychiatric/Behavioral Disturbances

Psychiatric/behavioral disturbances (e.g., depression, mood) were dose-related for both the adjunctive epilepsy and migraine populations treated with topiramate [see Warnings and Precautions (5.6)].

Somnolence/Fatigue

Somnolence and fatigue were the adverse reactions most frequently reported during clinical trials of topiramate for adjunctive epilepsy. For the adjunctive epilepsy population, the incidence of fatigue was dose-related. For the monotherapy epilepsy population, the incidence of somnolence was dose-related. For the migraine population, the incidences of both somnolence and fatigue were dose-related and more common in the titration phase.

Pediatric Patients

In pediatric epilepsy trials (adjunctive and monotherapy) conducted with topiramate, the incidence of cognitive/neuropsychiatric adverse reactions in pediatric patients was generally lower than that observed in adults. These reactions included psychomotor slowing, difficulty with concentration/attention, speech disorders/related speech problems and language problems. The most frequently reported neuropsychiatric reactions in pediatric epilepsy patients during adjunctive therapy double-blind studies were somnolence and fatigue. The most frequently reported cognitive/neuropsychiatric reactions in pediatric epilepsy patients in the 50 mg/day and 400 mg/day groups during the monotherapy double-blind study were headache, dizziness, anorexia, and somnolence.

In pediatric migraine patients, the incidence of cognitive/neuropsychiatric adverse reactions was increased in immediate-release topiramate-treated patients compared to placebo.

The risk for cognitive/neuropsychiatric adverse reactions was dose-dependent, and was greatest at the highest dose (200 mg). This risk for cognitive/neuropsychiatric adverse reactions was also greater in younger patients (6 to 11 years of age) than in older patients (12 to 17 years of age). The most common cognitive/neuropsychiatric adverse reaction in these trials was difficulty with concentration/attention. Cognitive adverse reactions most commonly developed during titration and sometimes persisted for various durations after completion of titration. The Cambridge Neuropsychological Test Automated Battery (CANTAB) was administered to adolescents (12 to 17 years of age) to assess the effects of topiramate on cognitive function at baseline at the end of the Study 3 [see Clinical Studies (14.4)]. Mean change from baseline in certain CANTAB tests suggests that topiramate treatment may result in psychomotor slowing and decreased verbal fluency.

5.8 Fetal Toxicity

TROKENDI XR can cause fetal harm when administered to a pregnant woman. Data from pregnancy registries indicate that infants exposed to topiramate in uterohave an increased risk of major congenital malformations, including but not limited to cleft lip and/or cleft palate (oral clefts), and of being small for gestational age (SGA). When multiple species of pregnant animals received topiramate at clinically relevant doses, structural malformations, including craniofacial defects, and reduced fetal weights occurred in offspring [see Use in Specific Populations (8.1)] .

Consider the benefits and risks of TROKENDI XR®when administering the drug in women of childbearing potential, particularly when TROKENDI XR®is considered for a condition not usually associated with permanent injury or death [see Use in Specific Populations (8.1)] . TROKENDI XR®should be used during pregnancy only if the potential benefit outweighs the potential risk. If this drug is used during pregnancy, or if the patient becomes pregnant while taking this drug, the patient should be informed of the potential hazard to a fetus [see Use in Specific Populations (8.1)] .

5.9 Withdrawal of Antiepileptic Drugs

In patients with or without a history of seizures or epilepsy, antiepileptic drugs, including TROKENDI XR®, should be gradually withdrawn to minimize the potential for seizures or increased seizure frequency [see Clinical Studies (14)] . In situations where rapid withdrawal of TROKENDI XR®is medically required, appropriate monitoring is recommended.

5.10 Decrease in Bone Mineral Density

Results of a one-year active-controlled study in pediatric patients (N=63) demonstrated negative effects of immediate-release topiramate monotherapy on bone mineral acquisition via statistically significant decreases in bone mineral density (BMD) measured in lumbar spine and in total body less head [see Use in Specific Populations (8.4)]. Twenty-one percent of immediate-release topiramate-treated patients experienced clinically important reductions in BMD (Z score change from baseline of -0.5 or greater) compared to 0 patients in the control group. Although decreases in BMD occurred across all pediatric age subgroups, patients 6 to 9 years of age were most commonly affected. The sample size and study duration were too small to determine if fracture risk is increased. Decreased BMD in the lumbar spine was correlated with decreased serum bicarbonate, which commonly occurs with topiramate treatment and reflects metabolic acidosis, a known cause of increased bone resorption [see Warnings and Precautions (5.4)]. Although small decreases in some markers of bone metabolism (e.g., serum alkaline phosphatase, calcium, phosphorus, and 1,25-dihydroxyvitamin D) occurred in immediate-release topiramate-treated patients, more significant decreases in serum parathyroid hormone and 25-hydroxyvitamin D, hormones involved in bone metabolism, were observed, along with an increased excretion of urinary calcium.

5.11 Negative Effects on Growth (Height and Weight)

Results of a one-year active-controlled study of pediatric patients (N=63) demonstrated negative effects of immediate-release topiramate monotherapy on growth (i.e., height and weight) [see Use in Specific Populations (8.4)]. Although continued growth was observed in both treatment groups, the immediate-release topiramate group showed statistically significant reductions in mean annual change from baseline in body weight compared to the control group. A similar trend of attenuation in height velocity and height change from baseline was also observed in the immediate-release topiramate group compared to the control group. Negative effects on weight and height were seen across all immediate-release topiramate age subgroups. Growth (height and weight) of children receiving prolonged TROKENDI XR®therapy should be carefully monitored.

5.12 Serious Skin Reactions

Serious skin reactions (Stevens-Johnson Syndrome [SJS] and Toxic Epidermal Necrolysis [TEN]) have been reported in patients receiving topiramate. TROKENDI XR should be discontinued at the first sign of a rash, unless the rash is clearly not drug-related. If signs or symptoms suggest SJS/TEN, use of this drug should not be resumed and alternative therapy should be considered. Inform patients about the signs of serious skin reactions.

5.13 Hyperammonemia and Encephalopathy (Without and With Concomitant Valproic Acid Use)

Topiramate treatment can cause hyperammonemia with or without encephalopathy [see Adverse Reactions (6.2)] . The risk for hyperammonemia with topiramate appears dose-related. Hyperammonemia has been reported more frequently when topiramate is used concomitantly with valproic acid. Postmarketing cases of hyperammonemia with or without encephalopathy have been reported with topiramate and valproic acid in patients who previously tolerated either drug alone [see Drug Interactions (7.2)] .

Clinical symptoms of hyperammonemic encephalopathy often include acute alterations in level of consciousness and/or cognitive function with lethargy and/or vomiting. In most cases, hyperammonemic encephalopathy abated with discontinuation of treatment.

The incidence of hyperammonemia in pediatric patients 12 to 17 years of age in the preventive treatment of migraine trials was 26% in patients taking topiramate monotherapy at 100 mg/day, and 14% in patients taking topiramate at 50 mg/day, compared to 9% in patients taking placebo. There was also an increased incidence of markedly increased hyperammonemia at the 100 mg dose.

Dose-related hyperammonemia was also seen in pediatric patients 1 to 24 months of age treated with topiramate and concomitant valproic acid for partial onset epilepsy, and this was not due to a pharmacokinetic interaction.

In some patients, hyperammonemia can be asymptomatic.

Monitoring for Hyperammonemia

Patients with inborn errors of metabolism or reduced hepatic mitochondrial activity may be at an increased risk for hyperammonemia with or without encephalopathy. Although not studied, topiramate or TROKENDI XR®treatment or an interaction of concomitant topiramate-based product and valproic acid treatment may exacerbate existing defects or unmask deficiencies in susceptible persons.

In patients who develop unexplained lethargy, vomiting, or changes in mental status associated with any topiramate treatment, hyperammonemic encephalopathy should be considered and an ammonia level should be measured.

5.14 Kidney Stones

Topiramate increases the risk of kidney stones. During adjunctive epilepsy trials, the risk for kidney stones in immediate-release topiramate-treated adults was 1.5%, an incidence about 2 to 4 times greater than expected in a similar, untreated population. As in the general population, the incidence of stone formation among topiramate-treated patients was higher in men. Kidney stones have also been reported in pediatric patients taking topiramate for epilepsy or migraine. During long-term (up to 1 year) topiramate treatment in an open-label extension study of 284 pediatric patients 1-24 months old with epilepsy, 7% developed kidney or bladder stones. TROKENDI XR®would be expected to have the same effect as immediate-release topiramate on the formation of kidney stones. TROKENDI XR®is not approved for treatment of epilepsy in pediatric patients less than 6 years old [see Use in Specific Populations (8.4)] .

Topiramate is a carbonic anhydrase inhibitor. Carbonic anhydrase inhibitors can promote stone formation by reducing urinary citrate excretion and by increasing urinary pH [see Warnings and Precautions (5.4)] . The concomitant use of TROKENDI XR®with any other drug producing metabolic acidosis, or potentially in patients on a ketogenic diet, may create a physiological environment that increases the risk of kidney stone formation, and should therefore be avoided.

Increased fluid intake increases the urinary output, lowering the concentration of substances involved in stone formation. Hydration is recommended to reduce new stone formation.

An increase in urinary calcium and a marked decrease in urinary citrate was observed in immediate-release topiramate-treated pediatric patients in a one-year active-controlled study [see Use in Specific Populations (8.4)]. This increased ratio of urinary calcium/citrate increases the risk of kidney stones and/or nephrocalcinosis.

5.15 Hypothermia With Concomitant Valproic Acid Use

Hypothermia, defined as a drop in body core temperature to < 35°C (95°F), has been reported in association with topiramate use with concomitant valproic acid (VPA) both in conjunction with and in the absence of hyperammonemia. This adverse reaction in patients using concomitant topiramate and valproate can occur after starting topiramate treatment or after increasing the daily dose of topiramate [see Drug Interactions (7.2)] . Consideration should be given to stopping TROKENDI XR or valproate in patients who develop hypothermia, which may be manifested by a variety of clinical abnormalities including lethargy, confusion, coma, and significant alterations in other major organ systems such as the cardiovascular and respiratory systems. Clinical management and assessment should include examination of blood ammonia levels.

6 ADVERSE REACTIONS

The following serious adverse reactions are discussed in more detail in other sections of the labeling:

- Acute Myopia and Secondary Angle Closure Glaucoma [see Warnings and Precautions (5.1)]
- Visual Field Defects [see Warnings and Precautions 5.2]
- Oligohydrosis and Hyperthermia [see Warnings and Precautions (5.3)]
- Metabolic Acidosis [see Warnings and Precautions (5.4)]
- Interaction With Alcohol [see Warnings and Precautions (5.5)]
- Suicidal Behavior and Ideation [see Warnings and Precautions (5.6)]
- Cognitive/Neuropsychiatric Adverse Reactions [see Warnings and Precautions (5.7)]
- Fetal Toxicity [see Warnings and Precautions (5.8)]
- Withdrawal of Antiepileptic Drugs [see Warnings and Precautions (5.9)]
- Decrease of Bone Mineral Density [see Warnings and Precautions (5.10)]
- Negative Effects on Growth (Height and Weight) [see Warnings and Precautions (5.11)]
- Serious Skin Reactions [see Warnings and Precautions (5.12)]
- Hyperammonemia and Encephalopathy (Without and With Concomitant Valproic Acid Use) [see Warnings and Precautions (5.13)]
- Kidney Stones [see Warnings and Precautions (5.14)]
- Hypothermia With Concomitant Valproic Acid Use [see Warnings and Precautions (5.15)]

The data described in the following sections were obtained using immediate-release topiramate tablets. TROKENDI XR®has not been studied in a randomized, placebo-controlled Phase III clinical study; however, it is expected that TROKENDI XR®would produce a similar adverse reaction profile as immediate-release topiramate.

6.1 Clinical Trials Experience

Because clinical trials are conducted under widely varying conditions, adverse reaction rates observed in the clinical trials of a drug cannot be directly compared to rates in the clinical trials of another drug and may not reflect the rates observed in practice.

Monotherapy Epilepsy

Adults 16 Years of Age and Older

The most common adverse reactions in the controlled trial (Study 1) that occurred in adults in the 400 mg/day topiramate group and at an incidence higher (≥ 10%) than in the 50 mg per day group were: paresthesia, weight loss, and anorexia (see Table 3).

Approximately 21% of the 159 adult patients in the 400 mg/day group who received topiramate as monotherapy in Study 1 discontinued therapy due to adverse reactions. The most common (≥ 2% more frequent than low-dose 50 mg/day topiramate) adverse reactions causing discontinuation were difficulty with memory, fatigue, asthenia, insomnia, somnolence, and paresthesia.

Pediatric Patients 6 Years to 15 Years of Age

The most common adverse reactions in the controlled trial (Study 1) that occurred in pediatric patients in the 400 mg/day topiramate group and at an incidence higher (≥ 10%) than in the 50 mg/day group were fever and weight loss (see Table 3).

Approximately 14% of the 77 pediatric patients in the 400 mg/day group who received topiramate as monotherapy in the controlled clinical trial discontinued therapy due to adverse reactions. The most common (≥ 2% more frequent than in the 50 mg/day group) adverse reactions resulting in discontinuation in this trial were difficulty with concentration/attention, fever, flushing, and confusion.

Table 3 represents the incidence of adverse reactions occurring in at least 3% of adult and pediatric patients treated with 400 mg/day immediate-release topiramate and occurring with greater incidence than 50 mg/day topiramate.

Table 3: Adverse Reactions in the High Dose Group as Compared to the Low Dose Group, in Monotherapy Epilepsy Trial in Adult and Pediatric Patients
 | Age Group
 | Pediatric (6 to 15 Years) |  | Adult (Age ≥16 Years)
 | Immediate-release Topiramate Daily Dosage Group (mg/day)
 | 50 | 400 | 50 | 400
Body System/ Adverse Reaction | (N=74) % | (N=77) % | (N=160) % | (N=159) %
Body as a Whole-General Disorders
Asthenia | 0 | 3 | 4 | 6
Fever | 1 | 12
Leg pain |  |  | 2 | 3
Central & Peripheral Nervous System Disorders
Paresthesia | 3 | 12 | 21 | 40
Dizziness |  |  | 13 | 14
Ataxia |  |  | 3 | 4
Hypoesthesia |  |  | 4 | 5
Hypertonia |  |  | 0 | 3
Involuntary Muscle contraction | 0 | 3
Vertigo | 0 | 3
Gastro-intestinal System Disorders
Constipation |  |  | 1 | 4
Diarrhea | 8 | 9
Gastritis |  |  | 0 | 3
Dry mouth |  |  | 1 | 3
Liver and Biliary System Disorders
Increase in Gamma-GT |  |  | 1 | 3
Metabolic and Nutritional Disorders
Weight loss | 7 | 17 | 6 | 17
Platelet, Bleeding & Clotting Disorders
Epistaxis | 0 | 4
Psychiatric Disorders
Anorexia |  |  | 4 | 14
Anxiety |  |  | 4 | 6
Cognitive problems | 1 | 6 | 1 | 4
Confusion | 0 | 3
Depression | 0 | 3 | 7 | 9
Difficulty with concentration or attention | 7 | 10 | 7 | 8
Difficulty with memory | 1 | 3 | 6 | 11
Insomnia |  |  | 8 | 9
Decrease in libido |  |  | 0 | 3
Mood problems | 1 | 8 | 2 | 5
Personality disorder (behavior problems) | 0 | 3
Psychomotor slowing |  |  | 3 | 5
Somnolence |  |  | 10 | 15
Red Blood Cell Disorders
Anemia | 1 | 3
Reproductive Disorders, Female
Intermenstrual bleeding | 0 | 3
Vaginal hemorrhage |  |  | 0 | 3
Resistance Mechanism Disorders
Infection | 3 | 8 | 2 | 3
Viral infection | 3 | 6 | 6 | 8
Respiratory System Disorders
Bronchitis | 1 | 5 | 3 | 4
Upper respiratory tract infection | 16 | 18
Rhinitis | 5 | 6 | 2 | 4
Sinusitis | 1 | 4
Skin and Appendages Disorders
Alopecia | 1 | 4 | 3 | 4
Pruritus |  |  | 1 | 4
Rash | 3 | 4 | 1 | 4
Acne |  |  | 2 | 3
Special Senses Other, Disorders
Taste perversion |  |  | 3 | 5
Urinary System Disorders
Cystitis |  |  | 1 | 3
Micturition frequency | 0 | 3 | 0 | 2
Renal calculus |  |  | 0 | 3
Urinary incontinence | 1 | 3
Vascular (Extracardiac) Disorders
Flushing | 0 | 5

Adjunctive Therapy Epilepsy

Adults 16 Years of Age and Older

In pooled controlled clinical trials in adults with partial-onset seizures, primary generalized tonic-clonic seizures, or Lennox-Gastaut syndrome, 183 patients received adjunctive therapy with immediate-release topiramate at dosages of 200 to 400 mg/day (recommended dosage range), and 291 patients received placebo. Patients in these trials were receiving 1 to 2 concomitant antiepileptic drugs in addition to immediate-release topiramate or placebo.

The most common adverse reactions in the controlled clinical trial that occurred in adult patients in the 200-400 mg/day topiramate group with an incidence higher (≥10%) than in the placebo group were: dizziness, speech disorders/related speech problems, somnolence, nervousness, psychomotor slowing, and vision abnormal (see Table 4) [see Clinical Studies (14.3)] .

Table 4 presents the incidence of adverse reactions occurring in at least 3% of adult patients treated with 200 to 400 mg/day topiramate and was greater than placebo incidence. The incidence of some adverse reactions (e.g., fatigue, dizziness, paresthesia, language problems, psychomotor slowing, depression, difficulty with concentration/attention, mood problems) was dose-related and much greater at higher than recommended topiramate dosing (i.e., 600 to 1000 mg/day) compared to the incidence of these adverse reactions at the recommended dosing (200 to 400 mg/day) range.

Table 4: Most Common Adverse Reactions in Pooled Placebo- Controlled, Adjunctive Epilepsy Trials in Adults [Patients in these adjunctive trials were receiving 1 to 2 concomitant antiepileptic drugs in addition to topiramate or placebo] , [Values represent the percentage of patients reporting a given reaction. Patient may have reported more than one adverse reaction during the study and can be included in more than one adverse reaction category.]
Body System/ | Placebo | Topiramate Dosage (mg/day) 200-400
Adverse Reaction | (N=291) % | (N=183) %
Body as a Whole-General Disorders
Fatigue | 13 | 15
Asthenia | 1 | 6
Back pain | 4 | 5
Chest pain | 3 | 4
Influenza-like symptoms | 2 | 3
Central & Peripheral Nervous System Disorders
Dizziness | 15 | 25
Ataxia | 7 | 16
Speech disorders/Related speech problems | 2 | 13
Paresthesia | 4 | 11
Nystagmus | 7 | 10
Tremor | 6 | 9
Language problems | 1 | 6
Coordination abnormal | 2 | 4
Gait abnormal | 1 | 3
Gastro-Intestinal System Disorders
Nausea | 8 | 10
Dyspepsia | 6 | 7
Abdominal pain | 4 | 6
Constipation | 2 | 4
Metabolic and Nutritional Disorders
Weight loss | 3 | 9
Psychiatric Disorders
Somnolence | 12 | 29
Nervousness | 6 | 16
Psychomotor slowing | 2 | 13
Difficulty with memory | 3 | 12
Confusion | 5 | 11
Anorexia | 4 | 10
Difficulty with concentration/attention | 2 | 6
Mood problems | 2 | 4
Agitation | 2 | 3
Aggressive reaction | 2 | 3
Emotional liability | 1 | 3
Cognitive problems | 1 | 3
Reproductive Disorders, Female
Breast pain | 2 | 4
Respiratory System Disorders
Rhinitis | 6 | 7
Pharyngitis | 2 | 6
Sinusitis | 4 | 5
Vision Disorders
Vision abnormal | 2 | 13
Diplopia | 5 | 10

In controlled clinical trials in adults, 11% of patients receiving immediate-release topiramate 200 to 400 mg per day as adjunctive therapy discontinued due to adverse reactions. This rate appeared to increase at dosages above 400 mg per day. Adverse reactions associated with discontinuing therapy included somnolence, dizziness, anxiety, difficulty with concentration or attention, fatigue, and paresthesia.

Pediatric Patients 2 to 15 Years of Age

In pooled, controlled clinical trials in pediatric patients (2 to 15 years of age) with partial-onset seizures, primary generalized tonic-clonic seizures, or Lennox-Gastaut syndrome, 98 patients received adjunctive therapy with immediate-release topiramate at dosages of 5 mg to 9 mg/kg/day (recommended dosage range) and 101 patients received placebo.

The most common adverse reactions in the controlled clinical trial that occurred in pediatric patients in the 5 mg to 9 mg/kg/day immediate-release topiramate group with an incidence higher (≥10%) than in the placebo group were: fatigue and somnolence (see Table 5).

Table 5 presents the incidence of adverse reactions that occurred in at least 3% of pediatric patients 2 to 15 years of age receiving 5 mg to 9 mg/kg/day (recommended dosage range) of immediate-release topiramate and was greater than placebo incidence.

Table 5: Adverse Reactions in Pooled Placebo-Controlled, Adjunctive Epilepsy Trial in Pediatric Patients 2 to 15 Years of Age [Patients in these adjunctive trials were receiving 1 to 2 concomitant antiepileptic drugs in addition to topiramate or placebo] , [Values represent the percentage of patients reporting a given adverse reaction. Patients may have reported more than one adverse reaction during the study and can be included in more than one adverse reaction category]
Body System/ Adverse Reaction | Placebo (N=101) % | Topiramate (N=98) %
Body as a Whole-General Disorders
Fatigue | 5 | 16
Injury | 13 | 14
Central & Peripheral Nervous System Disorders
Gait abnormal | 5 | 8
Ataxia | 2 | 6
Hyperkinesia | 4 | 5
Dizziness | 2 | 4
Speech disorders/Related speech problems | 2 | 4
Gastro-Intestinal System Disorders
Nausea | 5 | 6
Saliva increased | 4 | 6
Constipation | 4 | 5
Gastroenteritis | 2 | 3
Metabolic and Nutritional Disorders
Weight loss | 1 | 9
Platelet, Bleeding & Clotting Disorders
Purpura | 4 | 8
Epistaxis | 1 | 4
Psychiatric Disorders
Somnolence | 16 | 26
Anorexia | 15 | 24
Nervousness | 7 | 14
Personality disorder (Behavior Problems) | 9 | 11
Difficulty with concentration/attention | 2 | 10
Aggressive reaction | 4 | 9
Insomnia | 7 | 8
Difficulty with memory | 0 | 5
Confusion | 3 | 4
Psychomotor slowing | 2 | 3
Resistance Mechanism Disorders
Infection viral | 3 | 7
Respiratory System Disorders
Pneumonia | 1 | 5
Skin and Appendages Disorders
Skin Disorder | 2 | 3
Urinary System Disorders
Urinary incontinence | 2 | 4

None of the pediatric patients who received topiramate adjunctive therapy at 5 mg/kg/day to 9 mg/kg/day in controlled clinical trials discontinued due to adverse reactions.

Migraine

Adults

In the four multicenter, randomized, double-blind, placebo-controlled, parallel group clinical trials for the preventive treatment of migraine (which included 35 pediatric patients 12 to 15 years of age), most adverse reactions occurred more frequently during the titration period than during the maintenance period.

The most common adverse reactions with immediate-release topiramate 100mg in the clinical trials for the preventive treatment of migraine of predominantly adults that were seen at an incidence higher (≥5%) than in the placebo group were: paresthesia, anorexia, weight loss, taste perversion, diarrhea, difficulty with memory, hypoesthesia, and nausea (see Table 6).

Table 6 includes those adverse reactions that occurred in the placebo-controlled trials where the incidence in any immediate-release topiramate group was at least 3% and was greater than that for placebo patients. The incidence of some adverse reactions (e.g., fatigue, dizziness, somnolence, difficulty with memory, difficulty with concentration/attention) was dose-related and greater at higher than recommended topiramate dosing (200 mg/day) compared to the incidence of these adverse reactions at the recommended dosing (100 mg/day).

Table 6: Adverse Reactions in Pooled, Placebo-Controlled, Migraine Trials in Adults [Includes 35 adolescent patients age 12 to 15 years] , [Values represent the percentage of patients reporting a given reaction. Patients may have reported more than one adverse reaction during the study and can be included in more than one adverse reaction category.] , [Blurred vision was the most common term considered as vision abnormal. Blurred vision was an included term that accounted for more than 50% of reactions coded as vision abnormal, a preferred term]
 |  | Topiramate Dosage (mg/day)
Body System/ Adverse Reaction | Placebo (N=445) % | 50 (N=235) % | 100 (N=386) %
Body as a Whole-General Disorders
Fatigue | 11 | 14 | 15
Injury | 7 | 9 | 6
Central & Peripheral Nervous System Disorders
Paresthesia | 6 | 35 | 51
Dizziness | 10 | 8 | 9
Hypoaesthesia | 2 | 6 | 7
Language problems | 2 | 7 | 6
Gastro-Intestinal System Disorders
Nausea | 8 | 9 | 13
Diarrhea | 4 | 9 | 11
Abdominal pain | 5 | 6 | 6
Dyspepsia | 3 | 4 | 5
Dry mouth | 2 | 2 | 3
Gastroenteritis | 1 | 3 | 3
Metabolic and Nutritional Disorders
Weight loss | 1 | 6 | 9
Musculoskeletal System Disorders
Arthralgia | 2 | 7 | 3
Psychiatric Disorders
Anorexia | 6 | 9 | 15
Somnolence | 5 | 8 | 7
Difficulty with memory | 2 | 7 | 7
Insomnia | 5 | 6 | 7
Difficulty with concentration/attention | 2 | 3 | 6
Mood problems | 2 | 3 | 6
Anxiety | 3 | 4 | 5
Depression | 4 | 3 | 4
Nervousness | 2 | 4 | 4
Confusion | 2 | 2 | 3
Psychomotor slowing | 1 | 3 | 2
Reproductive Disorders, Female
Menstrual disorder | 2 | 3 | 2
Reproductive Disorders, Male
Ejaculation premature | 0 | 3 | 0
Resistance Mechanism Disorders
Viral Infection | 3 | 4 | 4
Respiratory System Disorders
Upper respiratory tract infection | 12 | 13 | 14
Sinusitis | 6 | 10 | 6
Pharyngitis | 4 | 5 | 6
Coughing | 2 | 2 | 4
Bronchitis | 2 | 3 | 3
Dyspnea | 2 | 1 | 3
Skin and Appendages Disorders
Pruritis | 2 | 4 | 2
Special Sense Other, Disorders
Taste perversion | 1 | 15 | 8
Urinary System Disorders
Urinary tract infection | 2 | 4 | 2
Vision Disorders
Blurred vision | 2 | 4 | 2

Of the 1135 patients exposed to immediate-release topiramate in the adult placebo-controlled studies, 25% discontinued due to adverse reactions, compared to 10% of the 445 placebo patients. The adverse reactions associated with discontinuing therapy in the immediate-release topiramate-treated patients in these studies included paresthesia (7%), fatigue (4%), nausea (4%), difficulty with concentration/attention (3%), insomnia (3%), anorexia (2%), and dizziness (2%).

Patients treated in these studies experienced mean percent reductions in body weight that were dose-dependent. This change was not seen in the placebo group. Mean changes of 0%, -2%, -3%, and -4% were seen for the placebo group, immediate-release topiramate 50 mg, 100 mg, and 200 mg groups, respectively.

Pediatric Patients 12 to 17 Years of Age

In five randomized, double-blind, placebo-controlled, parallel group clinical trials for the preventive treatment of migraine, most of the adverse reactions occurred more frequently during the titration period than during the maintenance period. Among adverse reactions with onset during titration, approximately half persisted into the maintenance period.

In four, fixed-dose, double-blind clinical trials for the preventive treatment of migraine in pediatric patients 12 to 17 years of age, the most common adverse reactions with immediate-release topiramate 100 mg that were seen at an incidence higher (≥5%) than in the placebo group were: paresthesia, upper respiratory tract infection, anorexia, and abdominal pain (see Table 7). Table 7 shows adverse reactions from the pediatric trial (Study 13 [see Clinical Studies (14.4)]) in which 103 pediatric patients were treated with placebo or 50 mg or 100 mg of immediate-release topiramate, and three predominantly adult trials in which 49 pediatric patients (12 to 17 years of age) were treated with placebo or 50 mg, 100 mg, or 200 mg of immediate-release topiramate [see Clinical Studies (14.4)]. Table 7 also shows adverse reactions in pediatric patients in controlled migraine trials when the incidence in an immediate-release topiramate dose group was at least 5% or higher and greater than the incidence of placebo. Many adverse reactions shown in Table 7 indicate a dose-dependent relationship. The incidence of some adverse reactions (e.g., allergy, fatigue, headache, anorexia, insomnia, somnolence, and viral infection) was dose-related and greater at higher than recommended immediate-release topiramate dosing (200 mg daily) compared to the incidence of these adverse reactions at the recommended dosing (100 mg daily).

Table 7: Adverse Reactions in Pooled Double-Blind Studies for the Preventive Treatment of Migraine in Pediatric Patients 12 to 17 Years of Age) [35 adolescent patients aged 12 to <16 years were also included in adverse reaction assessment for adults] [Incidence is based on the number of subjects experiencing at least 1 adverse event, not the number of events.]
 |  | Immediate-Release Topiramate Dosage
Body System/ Adverse Reaction | Placebo (N=45) % | 50 mg/day (N=46) % | 100 mg/day (N=48) %
Body as a Whole – General Disorders
Fatigue | 7 | 7 | 8
Fever | 2 | 4 | 6
Central & Peripheral Nervous System Disorders
Paresthesia | 7 | 20 | 19
Dizziness | 4 | 4 | 6
Gastrointestinal System Disorders
Abdominal pain | 9 | 7 | 15
Nausea | 4 | 4 | 8
Metabolic and Nutritional Disorders
Weight loss | 2 | 7 | 4
Psychiatric Disorders
Anorexia | 4 | 9 | 10
Somnolence | 2 | 2 | 6
Insomnia | 2 | 9 | 2
Resistance Mechanism Disorders
Infection viral | 4 | 4 | 8
Respiratory System Disorders
Upper respiratory tract infection | 11 | 26 | 23
Rhinitis | 2 | 7 | 6
Sinusitis | 2 | 9 | 4
Coughing | 0 | 7 | 2
Special Senses Other, Disorders
Taste perversion | 2 | 2 | 6
Vision Disorders
Conjunctivitis | 4 | 7 | 4

In the double-blind placebo-controlled studies, adverse reactions led to discontinuation of treatment in 8% of placebo patients compared with 6% of immediate-release topiramate-treated patients. Adverse reactions associated with discontinuing therapy that occurred in more than one immediate-release topiramate-treated patient were fatigue (1%), headache (1%), and somnolence (1%).

Increased Risk for Bleeding

Topiramate is associated with an increased risk for bleeding. In a pooled analysis of placebo-controlled studies of approved and unapproved indications, bleeding was more frequently reported as an adverse reaction for topiramate than for placebo (4.5% versus 3.0% in adult patients, and 4.4% versus 2.3% in pediatric patients). In this analysis, the incidence of serious bleeding events for topiramate and placebo was 0.3% versus 0.2% for adult patients, and 0.4% versus 0% for pediatric patients.

Adverse bleeding reactions reported with topiramate ranged from mild epistaxis, ecchymosis, and increased menstrual bleeding to life-threatening hemorrhages. In patients with serious bleeding events, conditions that increased the risk for bleeding were often present, or patients were often taking drugs that cause thrombocytopenia (other antiepileptic drugs) or affect platelet function or coagulation (e.g., aspirin, nonsteroidal anti-inflammatory drugs, selective serotonin reuptake inhibitors, or warfarin or other anticoagulants).

Other Adverse Reactions Observed During Clinical Trials

Other adverse reactions seen during clinical trials were: abnormal coordination, eosinophilia, gingival bleeding, hematuria, hypotension, myalgia, myopia, postural hypotension, scotoma, suicide attempt, syncope, and visual field defect.

Laboratory Test Abnormalities

Adult Patients

In addition to changes in serum bicarbonate (i.e., metabolic acidosis), sodium chloride, and ammonia, immediate-release topiramate was associated with changes in several clinical laboratory analytes in randomized, double-blind, placebo-controlled studies [see Warnings and Precautions (5.4, 5.13)] . Controlled trials of adjunctive topiramate treatment of adults for partial-onset seizures showed an increased incidence of markedly decreased serum phosphorus (6% topiramate versus 2% placebo), markedly increased serum alkaline phosphatase (3% topiramate versus 1% placebo), and decreased serum potassium (0.4% topiramate versus 0.1% placebo).

Pediatric Patients

In pediatric patients (1-24 months) receiving adjunctive topiramate for partial-onset seizures, there was an increased incidence for an increased result (relative to normal analyte reference range) associated with immediate-release topiramate (vs placebo) for the following clinical laboratory analytes: creatinine, BUN, alkaline phosphatase, and total protein. The incidence was also increased for a decreased result for bicarbonate (i.e., metabolic acidosis) and potassium with immediate-release topiramate (vs. placebo) [see Use in Specific Populations (8.4)] . TROKENDI XR®is not indicated for partial-onset seizures in pediatric patients less than 6 years of age.

In pediatric patients (ranging from 6-17 years of age) receiving immediate-release topiramate for the preventive treatment of migraine, there was an increased incidence for an increased result (relative to normal analyte reference range) associated with immediate-release topiramate (vs placebo) for the following clinical laboratory analytes: creatinine, BUN, uric acid, chloride, ammonia, alkaline phosphatase, total protein, platelets, and eosinophils. The incidence was also increased for a decreased result for phosphorus, bicarbonate, total white blood count, and neutrophils [see Use in Specific Populations (8.4)]. TROKENDI XR®is not indicated for the preventive treatment of migraine in pediatric patients less than 12 years of age.

6.2 Postmarketing Experience

The following adverse reactions have been identified during post-approval use of immediate-release topiramate. Because these reactions are reported voluntarily from a population of uncertain size, it is not always possible to reliably estimate their frequency or establish a causal relationship to drug exposure.

Body as a Whole-General Disorders: oligohydrosis and hyperthermia [see Warnings and Precautions (5.3)] , hyperammonemia, hyperammonemic encephalopathy [see Warnings and Precautions (5.13)] , hypothermia with concomitant valproic acid [see Warnings and Precautions 5.15)] .

Gastrointestinal System Disorders: hepatic failure (including fatalities), hepatitis, pancreatitis

Skin and Appendage Disorders: bullous skin reactions (including erythema multiforme, Stevens-Johnson syndrome, toxic epidermal necrolysis) [see Warnings and Precautions (5.12)] , pemphigus

Urinary System Disorders: kidney stones, nephrocalcinosis [see Warnings and Precautions (5.14)]

Vision disorders: acute myopia, secondary angle closure glaucoma [see Warnings and Precautions (5.1)], maculopathy

Hematological Disorders: decrease of the International Normalized Ratio (INR) or prothrombin time when given concomitantly with vitamin K antagonist anticoagulant medications such as warfarin.

7 DRUG INTERACTIONS

7.1 Alcohol

Alcohol use is contraindicated within 6 hours prior to and 6 hours after TROKENDI XR®administration [see Contraindications (4)and Warnings and Precautions (5.5)].

7.2 Antiepileptic Drugs

Concomitant administration of phenytoin or carbamazepine with topiramate resulted in a clinically significant decrease in plasma concentrations of topiramate when compared to topiramate given alone. A dosage adjustment may be needed [see Dosage and Administration (2.1), Clinical Pharmacology (12.3)].

Concomitant administration of valproic acid and topiramate has been associated with hypothermia and hyperammonemia with and without encephalopathy. Examine blood ammonia levels in patients in whom the onset of hypothermia has been reported [see Warnings and Precautions (5.13, 5.15)and Clinical Pharmacology (12.3)] .

7.3 Other Carbonic Anhydrase Inhibitors

Concomitant use of topiramate, a carbonic anhydrase inhibitor, with any other carbonic anhydrase inhibitor (e.g., zonisamide or acetazolamide) may increase the severity of metabolic acidosis and may also increase the risk of kidney stone formation. Patients should be monitored for the appearance or worsening of metabolic acidosis when TROKENDI XR®is given concomitantly with another carbonic anhydrase inhibitor [see Clinical Pharmacology (12.3)].

7.4 CNS Depressants

Concomitant administration of topiramate with other CNS depressant drugs or alcohol has not been evaluated in clinical studies. Because of the potential of topiramate to cause CNS depression, as well as other cognitive and/or neuropsychiatric adverse reactions, TROKENDI XR®should be used with extreme caution if used in combination with alcohol and other CNS depressants [see Contraindications (4)and Warnings and Precautions (5.7)].

7.5 Contraceptives

The possibility of decreased contraceptive efficacy and increased breakthrough bleeding may occur in patients taking contraceptive products with TROKENDI XR®. Patients taking estrogen-containing or progestin-only contraceptives should be asked to report any change in their bleeding patterns. Contraceptive efficacy can be decreased even in the absence of breakthrough bleeding [see Clinical Pharmacology (12.3)] .

7.6 Hydrochlorothiazide (HCTZ)

Topiramate Cmaxand AUC increased when HCTZ was added to immediate-release topiramate. The clinical significance of this change is unknown. The addition of HCTZ to TROKENDI XR®may require a decrease in the TROKENDI XR®dose [see Clinical Pharmacology (12.3)] .

7.7 Pioglitazone

A decrease in the exposure of pioglitazone and its active metabolites were noted with the concurrent use of pioglitazone and immediate-release topiramate in a clinical trial. The clinical relevance of these observations is unknown; however, when TROKENDI XR®is added to pioglitazone therapy or pioglitazone is added to TROKENDI XR®therapy, careful attention should be given to the routine monitoring of patients for adequate control of their diabetic disease state [see Clinical Pharmacology (12.3)] .

7.8 Lithium

An increase in systemic exposure of lithium following topiramate doses of up to 600 mg/day can occur. Lithium levels should be monitored when co-administered with high-dose TROKENDI XR® [see Clinical Pharmacology (12.3)].

7.9 Amitriptyline

Some patients may experience a large increase in amitriptyline concentration in the presence of TROKENDI XR®and any adjustments in amitriptyline dose should be made according to the patients' clinical response and not on the basis of plasma levels [see Clinical Pharmacology (12.3)] .

8 USE IN SPECIFIC POPULATIONS

8.1 Pregnancy

Pregnancy Exposure Registry

There is a pregnancy exposure registry that monitors pregnancy outcomes in women exposed to antiepileptic drugs (AEDs), such as TROKENDI XR, during pregnancy. Patients should be encouraged to enroll in the North American Antiepileptic Drug (NAAED) Pregnancy Registry if they become pregnant. This registry is collecting information about the safety of antiepileptic drugs during pregnancy. To enroll, patients can call the toll-free number 1-888-233-2334. Information about the North American Drug Pregnancy Registry can be found at http://www.aedpregnancyregistry.org/.

Risk Summary

TROKENDI XR can cause fetal harm when administered to a pregnant woman. Data from pregnancy registries indicate that infants exposed to topiramate in uterohave increased risk of major congenital malformations, including but not limited to cleft lip and/or cleft palate (oral clefts), and of being small for gestational age (SGA) [see Human Data] . SGA has been observed at all doses and appears to be dose-dependent. The prevalence of SGA is greater in infants of women who received higher doses of topiramate during pregnancy. In addition, the prevalence of SGA in infants of women who continued topiramate use until later in pregnancy is higher compared to the prevalence in infants of women who stopped topiramate use before the third trimester.

In multiple animal species, topiramate demonstrated developmental toxicity, including increased incidences of fetal malformations, in the absence of maternal toxicity at clinically relevant doses [see Animal Data] .

All pregnancies have a background risk of birth defects, loss, or other adverse outcomes. The estimated background risk of major birth defects and miscarriage for the indicated population is unknown. In the U.S. general population, the estimated background risks of major birth defects and miscarriage in clinically recognized pregnancies are 2-4% and 15-20%, respectively.

Clinical Considerations

Fetal/Neonatal Adverse reactions

Consider the benefits and risks of topiramate when prescribing this drug to women of childbearing potential, particularly when topiramate is considered for a condition not usually associated with permanent injury or death. Because of the risk of oral clefts to the fetus, which occur in the first trimester of pregnancy before many women know they are pregnant, all women of childbearing potential should be informed of the potential risk to the fetus from exposure to topiramate. Women who are planning a pregnancy should be counseled regarding the relative risks and benefits of topiramate use during pregnancy, and alternative therapeutic options should be considered for these patients.

Labor or Delivery

Although the effect of topiramate on labor and delivery in humans has not been established, the development of topiramate-induced metabolic acidosis in the mother and/or in the fetus might affect the fetus' ability to tolerate labor.

TROKENDI XR treatment can cause metabolic acidosis [see Warnings and Precautions (5.4)] . The effect of topiramate-induced metabolic acidosis has not been studied in pregnancy; however, metabolic acidosis in pregnancy (due to other causes) can cause decreased fetal growth, decreased fetal oxygenation, and fetal death, and may affect the fetus' ability to tolerate labor. Pregnant patients should be monitored for metabolic acidosis and treated as in the nonpregnant state [see Warnings and Precautions (5.4)] . Newborns of mothers treated with TROKENDI XR should be monitored for metabolic acidosis because of transfer of topiramate to the fetus and possible occurrence of transient metabolic acidosis following birth.

Based on limited information, topiramate has also been associated with pre-term labor and premature delivery.

Data

Human Data

Data from pregnancy registries indicate an increased risk of major congenital malformations, including but not limited to oral clefts in infants exposed to topiramate during the first trimester of pregnancy. Other than oral clefts, no specific pattern of major congenital malformations or grouping of major congenital malformation types were observed. In the NAAED pregnancy registry, when topiramate-exposed infants with only oral clefts were excluded, the prevalence of major congenital malformations (4.1%) was higher than that in infants exposed to a reference AED (1.8%) or in infants with mothers without epilepsy and without exposure to AEDs (1.1%). The prevalence of oral clefts among topiramate-exposed infants (1.4%) was higher than the prevalence in infants exposed to reference AEDs (0.3%), or the prevalence in infants with mothers without epilepsy and without exposure to AEDs (0.11%). It was also higher than the background prevalence in United States (0.17%) as estimated by the Centers for Disease Control and Prevention (CDC). The relative risk of oral clefts in topiramate-exposed pregnancies in the NAAED Pregnancy Registry was 12.5 (95% Confidence Interval=[CI] 5.9-26.37) as compared to the risk in a background population of untreated women. The UK Epilepsy and Pregnancy Register reported a prevalence of oral clefts among infants exposed to topiramate monotherapy (3.2%) that was 16 times higher than the background rate in the UK (0.2%).

Data from the NAAED pregnancy registry and a population-based birth registry cohort indicate that exposure to topiramate in uterois associated with an increased risk of SGA newborns (birth weight <10th percentile). In the NAAED pregnancy registry, 19.7% of topiramate-exposed newborns were SGA compared to 7.9% of newborns exposed to a reference AED, and 5.4% of newborns of mothers without epilepsy and without AED exposure. In the Medical Birth Registry of Norway (MBRN), a population-based pregnancy registry, 25% of newborns in the topiramate monotherapy exposure group were SGA compared to 9% in the comparison group who were unexposed to AEDs. The long-term consequences of the SGA findings are not known.

Animal Data

When topiramate (0, 20, 100, or 500 mg/kg/day) was administered orally to pregnant mice during the period of organogenesis, incidences of fetal malformations (primarily craniofacial defects) were increased at all doses. Fetal body weights and skeletal ossification were reduced at the highest dose tested in conjunction with decreased maternal body weight gain. A no-effect dose for embryofetal developmental toxicity in mice was not identified. The lowest dose tested, which was associated with an increased incidence of malformations, is less than the maximum recommended human dose (MRHD) for epilepsy (400 mg/day) or migraine (100 mg/day) on a body surface area (mg/m^2) basis.

In pregnant rats administered topiramate (0, 20, 100, and 500 mg/kg/day or 0, 0.2, 2.5, 30, and 400 mg/kg/day) orally during the period of organogenesis, the frequency of limb malformations (ectrodactyly, micromelia, and amelia) was increased in fetuses at 400 and 500 mg/kg/day. Embryotoxicity (reduced fetal body weights, increased incidences of structural variations) was observed at doses as low as 20 mg/kg/day. Clinical signs of maternal toxicity were seen at 400 mg/kg/day and above, and maternal body weight gain was reduced at doses of 100 mg/kg/day or greater. The no-effect dose (2.5 mg/kg/day) for embryofetal developmental toxicity in rats is less than the MRHD for epilepsy or migraine on a mg/m^2basis.

In pregnant rabbits administered topiramate (0, 20, 60, and 180 mg/kg/day or 0, 10, 35, and 120 mg/kg/day) orally during organogenesis, embryofetal mortality was increased at 35 mg/kg/day and an increased incidence of fetal malformations (primarily rib and vertebral malformations) was observed at 120 mg/kg/day. Evidence of maternal toxicity (decreased body weight gain, clinical signs, and/or mortality) was seen at 35 mg/kg/day and above. The no-effect dose (20 mg/kg/day) for embryofetal developmental toxicity in rabbits is equivalent to the MRHD for epilepsy and approximately 4 times the MRHD for migraine on a mg/m^2basis.

When topiramate (0, 0.2, 4, 20, and 100 mg/kg/day or 0, 2, 20, and 200 mg/kg/day) was administered orally to female rats during the latter part of gestation and throughout lactation, offspring exhibited decreased viability and delayed physical development at 200 mg/kg/day and reductions in pre-and/or postweaning body weight gain at 2 mg/kg/day and above. Maternal toxicity (decreased body weight gain, clinical signs) was evident at 100 mg/kg/day or greater.

In a rat embryofetal development study which included postnatal assessment of offspring, oral administration of topiramate (0, 0.2, 2.5, 30, and 400 mg/kg/day) to pregnant animals during the period of organogenesis resulted in delayed physical development in offspring at 400 mg/kg/day and persistent reductions in body weight gain in offspring at 30 mg/kg/day and higher. The no-effect dose (0.2 mg/kg/day) for pre- and postnatal developmental toxicity is less than the MRHD for epilepsy or migraine on a mg/m^2basis.

8.2 Lactation

Risk Summary

Topiramate is excreted in human milk [see Data]. The effects of topiramate on milk production are unknown. Diarrhea and somnolence have been reported in breastfed infants whose mothers receive topiramate treatment.

The developmental and health benefits of breastfeeding should be considered along with the mother's clinical need for TROKENDI XR and any potential adverse effects on the breastfed infant from TROKENDI XR or from the underlying maternal condition.

Data

Limited data from 5 women with epilepsy treated with topiramate during lactation showed drug levels in milk similar to those in maternal plasma.

8.3 Females and Males of Reproductive Potential

Contraception

Women of childbearing potential who are not planning a pregnancy should use effective contraception because of the risk of major congenital malformations, including oral clefts, and the risk of infants being SGA [see Drug Interactions (7.5)and Use in Specific Populations (8.1)] .

8.4 Pediatric Use

Seizures in Pediatric Patients 6 Years of Age and Older

The safety and effectiveness of TROKENDI XR®for treatment of partial onset seizures, primary generalized tonic-clonic seizures, or Lennox-Gastaut syndromes in pediatric patients at least 6 years of age is based on controlled trials with immediate-release topiramate [see Adverse Reactions (6.1), Clinical Studies (14.2, 14.3)] .

The adverse reactions in pediatric patients treated for partial onset seizure, primary generalized tonic-clonic seizures, or Lennox-Gastaut syndrome are similar to those seen in adults [see Warnings and Precautions (5)and Adverse Reactions (6)] .

These include, but are not limited to:

- oligohydrosis and hyperthermia [see Warnings and Precautions (5.3)]
- dose-related increased incidence of metabolic acidosis [see Warnings and Precautions (5.4)]
- dose-related increased incidence of hyperammonemia [see Warnings and Precautions (5.13)]

Not Recommended for Pediatric Patients Younger than 6 Years of Age

The safety and effectiveness of TROKENDI XR for treatment of partial-onset seizures, primary generalized tonic-clonic seizures, or Lennox-Gastaut syndromes in pediatric patients younger than 6 years of age has not been established.

Because the capsule must be swallowed whole, and may not be sprinkled on food, crushed or chewed, TROKENDI XR®is recommended only for children age 6 or older.

The following pediatric use information for adjunctive treatment for partial onset epilepsy in infants and toddlers (1 to 24 months) is based on studies conducted with immediate-release topiramate, which failed to demonstrate efficacy.

Safety and effectiveness of immediate-release topiramate in patients below the age of 2 years have not been established for the adjunctive therapy treatment of partial onset seizures, primary generalized tonic-clonic seizures, or seizures associated with Lennox-Gastaut syndrome. In a single randomized, double-blind, placebo-controlled investigational trial, the efficacy, safety, and tolerability of immediate-release topiramate oral liquid and sprinkle formulations as an adjunct to concurrent antiepileptic drug therapy in pediatric patients 1 to 24 months of age with refractory partial-onset seizures were assessed. After 20 days of double-blind treatment, immediate-release topiramate (at fixed doses of 5, 15, and 25 mg/kg per day) did not demonstrate efficacy compared with placebo in controlling seizures.

In general, the adverse reaction profile for immediate-release topiramate in this population was similar to that of older pediatric patients, although results from the above controlled study, and an open-label, long-term extension study in these pediatric patients 1 to 24 months old suggested some adverse reactions not previously observed in older pediatric patients and adults; i.e., growth/length retardation, certain clinical laboratory abnormalities, and other adverse reactions that occurred with a greater frequency and/or greater severity than had been recognized previously from studies in older pediatric patients or adults for various indications.

These very young pediatric patients appeared to experience an increased risk for infections (any topiramate dose 12%, placebo 0%) and of respiratory disorders (any topiramate dose 40%, placebo 16%). The following adverse reactions were observed in at least 3% of patients on immediate-release topiramate and were 3% to 7% more frequent than in patients on placebo: viral infection, bronchitis, pharyngitis, rhinitis, otitis media, upper respiratory infection, cough, and bronchospasm. A generally similar profile was observed in older pediatric patients [see Adverse Reactions (6.1)].

Immediate-release topiramate resulted in an increased incidence of patients with increased creatinine (any topiramate dose 5%, placebo 0%), BUN (any topiramate dose 3%, placebo 0%), and protein (any topiramate dose 34%, placebo 6%), and an increased incidence of decreased potassium (any topiramate dose 7%, placebo 0%). This increased frequency of abnormal values was not dose related. Creatinine was the only analyte showing a noteworthy increased incidence (topiramate 25 mg/kg/day 5%, placebo 0%) of a markedly abnormal increase [see Adverse Reactions (6.1)] . The significance of these findings is uncertain.

Immediate-release topiramate treatment also produced a dose-related increase in the percentage of patients who had a shift from normal at baseline to high/increased (above the normal reference range) in total eosinophil count at the end of treatment. The incidence of these abnormal shifts was 6 % for placebo, 10% for 5 mg/kg/day, 9% for 15 mg/kg/day, 14% for 25 mg/kg/day, and 11% for any topiramate dose [see Adverse Reactions (6.1)] . There was a mean dose-related increase in alkaline phosphatase. The significance of these findings is uncertain.

Topiramate produced a dose-related increased incidence of hyperammonemia [see Warnings and Precautions (5.13)] .

Treatment with immediate-release topiramate for up to 1 year was associated with reductions in Z SCORES for length, weight, and head circumference [see Warnings and Precautions (5.4)and Adverse Reactions (6)] .

In open-label, uncontrolled experience, increasing impairment of adaptive behavior was documented in behavioral testing over time in this population. There was a suggestion that this effect was dose-related. However, because of the absence of an appropriate control group, it is not known if this decrement in function was treatment related or reflects the patient's underlying disease (e.g., patients who received higher doses may have more severe underlying disease) [see Warnings and Precautions (5.7)] .

In this open-label, uncontrolled study, the mortality was 37 deaths/1000 patient years. It is not possible to know whether this mortality rate is related to immediate-release topiramate treatment, because the background mortality rate for a similar, significantly refractory, young pediatric population (1 month to 24 months) with partial epilepsy is not known.

Other Pediatric Studies

Topiramate treatment produced a dose-related increased shift in serum creatinine from normal at baseline to an increased value at the end of 4 months treatment in adolescent patients (ages 12 years to 16 years) in a double-blind, placebo-controlled study [see Adverse Reactions (6.1)] .

A one-year, active-controlled, open-label study with blinded assessments of bone mineral density (BMD) and growth in pediatric patients 4 to 15 years of age, including 63 patients with recent or new onset of epilepsy, was conducted to assess effects of immediate-release topiramate (N=28, 6-15 years of age) versus levetiracetam (N=35, 4-15 years of age) monotherapy on bone mineralization and on height and weight, which reflect growth. Effects on bone mineralization were evaluated via dual-energy X-ray absorptiometry and blood markers. Table 8 summarizes effects of immediate-release topiramate at 12 months for key safety outcomes including BMD, height, height velocity, and weight. All Least Square Mean values for immediate-release topiramate and the comparator were positive. Therefore, the Least Square Mean treatment differences shown reflect an immediate-release topiramate-induced attenuation of the key safety outcomes. Statistically significant effects were observed for decreases in BMD (and bone mineral content) in lumbar spine and total body less head and in weight. Subgroup analyses according to age demonstrated similar negative effects for all key safety outcomes (i.e., BMD, height, weight).

Table 8 Summary of Immediate-release Topiramate Treatment Difference Results at 12 Months for Key Safety Outcomes
Safety Parameter | Treatment Difference in Least Square Means (95 % Confidence Interval)
Annual Change in BMD Lumbar Spine (g/cm^2) |  | -0.036 | (-0.058, -0.014)
Annual Change in BMD TBLH [TBLH=total body less head] (g/cm^2) |  | -0.026 | (-0.039, -0.012)
Annual Change in Height (cm) (4-9 years, Primary Analysis Population for Height) [Whereas no patients were randomized to 2-5 year age subgroup for immediate-release topiramate, 5 patients (4-5 years) were randomized to the active control group.] |  | -0.84 | (-2.67, 0.99)
Annual Change in Height (cm) (4-15 years) |  | -0.75 | (-2.21, 0.71)
Annual Change in Height (cm) (10-15 years) |  | -1.01 | (-3.64, 1.61)
Height Velocity (cm/year) (4-9 years) |  | -1.00 | (-2.76, 0.76)
Height Velocity (cm/year) (4-15 years) |  | -0.98 | (-2.33, 0.37)
Height Velocity (cm/year) (10-15 years) |  | -0.96 | (-3.24, 1.32)
Annual Change in Weight (kg) |  | -2.05 | (-3.66, -0.45)

Metabolic acidosis (serum bicarbonate <20 mEq/L) was observed in all immediate-release topiramate-treated patients at some time in the study [see Warnings and Precautions (5.4)]. Over the whole study, 76% more immediate-release topiramate-treated patients experienced persistent metabolic acidosis (i.e., 2 consecutive visits with or final serum bicarbonate < 20 mEq/L) compared to levetiracetam-treated patients. Over the whole study, 35% more immediate-release topiramate-treated patients experienced a markedly abnormally low serum bicarbonate (i.e., absolute value <17 mEq/L and ≥ 5mEq/L decrease from pre-treatment), indicating the frequency of more severe metabolic acidosis, compared to levetiracetam-treated patients. The decrease in BMD at 12 months was correlated with decreased serum bicarbonate, suggesting that metabolic acidosis was at least a partial factor contributing to this adverse effect on BMD.

Immediate-release topiramate-treated patients exhibited an increased risk for developing an increased serum creatinine and an increased serum glucose above the normal reference range compared to control patients.

Preventive Treatment of Migraine in Pediatric Patients 12 to 17 Years of Age

Safety and effectiveness of topiramate for the preventive treatment of migraine was studied in 5 double-blind, randomized, placebo-controlled, parallel-group trials in a total of 219 pediatric patients, at doses of 50 mg/day to 200 mg/day, or 2 to 3 mg/kg/day. These comprised a fixed dose study in 103 pediatric patients 12 to 17 years of age [see Clinical Studies (14.4)], a flexible dose (2 to 3 mg/kg/day), placebo-controlled study in 157 pediatric patients 6 to 16 years of age (including 67 pediatric patients 12 to 16 years of age), and a total of 49 pediatric patients 12 to 17 years of age in 3 studies for the preventive treatment of migraine primarily in adults. Open-label extension phases of 3 studies enabled evaluation of long-term safety for up to 6 months after the end of the double-blind phase.

Efficacy of topiramate for the preventive treatment of migraine in pediatric patients 12 to 17 years of age is demonstrated for a 100 mg daily dose in Study 3 [see Clinical Studies (14.4)]. Efficacy of topiramate (2 to 3 mg/kg/day) for the preventive treatment of migraine was not demonstrated in a placebo-controlled trial of 157 pediatric patients (6 to 16 years of age) that included treatment of 67 pediatric patients 12 to 16 years of age) for 20 weeks.

In the pediatric trials (12 to 17 years of age) in which patients were randomized to placebo or a fixed daily dose of immediate-release topiramate, the most common adverse reactions with immediate-release topiramate that were seen at an incidence higher (≥5%) than in the placebo group were: paresthesia, upper respiratory tract infection, anorexia, and abdominal pain [see Adverse Reactions (6.1)] .

The most common cognitive adverse reaction in pooled double-blind studies in pediatric patients 12 to 17 years of age was difficulty with concentration/attention [see Warnings and Precautions (5.7)] .

Markedly abnormally low serum bicarbonate values indicative of metabolic acidosis were reported in topiramate-treated pediatric migraine patients [see Warnings and Precautions (5.4)] .

In topiramate-treated pediatric patients (12 to 17 years of age) compared to placebo-treated patients, abnormally increased results were more frequent for creatinine, BUN, uric acid, chloride, ammonia, total protein, and platelets. Abnormally decreased results were observed with topiramate vs placebo treatment for phosphorus and bicarbonate [see Adverse Reactions (6.1)] .

Notable changes (increases and decreases) from baseline in systolic blood pressure, diastolic blood pressure, and pulse that were observed occurred more commonly in pediatric patients treated with topiramate compared to pediatric patients treated with placebo [see Clinical Pharmacology (12.2)] .

Preventive Treatment of Migraine in Pediatric Patients 6 to 11 Years of Age

Safety and effectiveness in pediatric patients below the age of 12 years have not been established for the preventive treatment of migraine.

In a double-blind study in 90 pediatric patients 6 to 11 years of age (including 59 topiramate-treated and 31 placebo patients), the adverse reaction profile was generally similar to that seen in pooled double-blind studies of pediatric patients 12 to 17 years of age. The most common adverse reactions that occurred in immediate-release topiramate-treated pediatric patients 6 to 11 years of age, and at least twice as frequently than placebo, were gastroenteritis (12% topiramate, 6% placebo), sinusitis (10% topiramate, 3% placebo), weight loss (8% topiramate, 3% placebo) and paresthesia (7% topiramate, 0% placebo). Difficulty with concentration/attention occurred in 3 topiramate-treated patients (5%) and 0 placebo-treated patients.

The risk for cognitive adverse reactions was greater in younger patients (6 to 11 years of age) than in older patients (12 to 17 years of age) [see Warnings and Precautions (5.7)] .

Juvenile Animal Studies

When topiramate (30, 90, and 300 mg/kg/day) was administered orally to rats during the juvenile period of development (postnatal days 12 to 50), bone growth plate thickness was reduced in males at the highest dose, which is approximately 5-8 times the maximum recommended pediatric dose (9 mg/kg/day) on a body surface area (mg/m^2) basis.

8.5 Geriatric Use

Clinical studies of immediate-release topiramate did not include sufficient numbers of subjects aged 65 and over to determine whether they respond differently than younger subjects. Dosage adjustment may be necessary for elderly with creatinine clearance less than 70 mL/min/1.73 m^2. Estimate GFR should be measured prior to dosing [see Dosage and Administration (2.5)and Clinical Pharmacology (12.3)] .

8.6 Renal Impairment

The clearance of topiramate is reduced in patients with moderate (creatinine clearance 30 to 69 mL/min/1.73m^2) and severe (creatinine clearance less than 30 mL/min/1.73m^2) renal impairment. A dosage adjustment is recommended in patients with moderate or severe renal impairment [see Dosage and Administration (2.5)and Clinical Pharmacology (12.3)] .

8.7 Patients Undergoing Hemodialysis

Topiramate is cleared by hemodialysis at a rate that is 4 to 6 times greater than in a normal individual. A dosage adjustment may be required [see Dosage and Administration (2.6)and Clinical Pharmacology (12.3)] .

10 OVERDOSAGE

Overdoses of topiramate have been reported. Signs and symptoms included convulsions, drowsiness, speech disturbance, blurred vision, diplopia, impaired mentation, lethargy, abnormal coordination, stupor, hypotension, abdominal pain, agitation, dizziness, and depression. The clinical consequences were not severe in most cases, but deaths have been reported after overdoses involving topiramate.

Topiramate overdose has resulted in severe metabolic acidosis [see Warnings and Precautions (5.4)] .

A patient who ingested a dose of immediate-release topiramate between 96 g and 110 g was admitted to a hospital with a coma lasting 20 to 24 hours followed by full recovery after 3 to 4 days.

Similar signs, symptoms, and clinical consequences are expected to occur with overdosage of TROKENDI XR®. In the event of overdose, TROKENDI XR®should be discontinued and general supportive treatment given until clinical toxicity has been diminished or resolved. Hemodialysis is an effective means of removing topiramate from the body.

11 DESCRIPTION

Topiramate, USP, is a sulfamate-substituted monosaccharide. TROKENDI XR®(topiramate) extended-release capsules are available as 25 mg, 50 mg, 100 mg, and 200 mg capsules for oral administration.

Topiramate is a white to off-white powder. Topiramate is freely soluble in polar organic solvents such as acetonitrile and acetone; and very slightly soluble to practically insoluble in non-polar organic solvents such as hexanes. Topiramate has the molecular formula C12H21NO8S and a molecular weight of 339.4. Topiramate is designated chemically as 2,3:4,5-Di- O-isopropylidene-β-D-fructopyranose sulfamate and has the following structural formula:

TROKENDI XR®(topiramate) is an extended-release capsule. TROKENDI XR®capsules contain the following inactive ingredients:

Sugar Spheres, NF
Hypromellose (Type 2910), USP
Mannitol, USP
Docusate Sodium, USP
Sodium Benzoate, NF
Ethylcellulose, NF
Oleic Acid, NF
Medium Chain Triglycerides, NF
Polyethylene Glycol, NF
Polyvinyl Alcohol, USP
Titanium Dioxide, USP
Talc, USP
Lecithin, NF
Xanthan Gum, NF
Glycerin, USP-NF

The capsule shells contain gelatin, USP; Titanium Dioxide, USP; and Colorants.

The colorants are:

FD&C Blue #1 (all strength capsules)
Yellow Iron Oxide, USP (25 mg and 50 mg capsules)
FD&C Red #3 (50 mg, 100 mg and 200 mg capsules)
FD&C Yellow #6 (50 mg, 100 mg and 200 mg capsules)
Riboflavin, USP (25 mg capsules)

All capsule shells are imprinted with black print that contains shellac, NF, and black iron oxide, NF.

12 CLINICAL PHARMACOLOGY

12.1 Mechanism of Action

The precise mechanisms by which topiramate exerts its anticonvulsant and preventive migraine effects are unknown; however, preclinical studies have revealed four properties that may contribute to topiramate's efficacy for epilepsy and the preventive treatment of migraine. Electrophysiological and biochemical evidence suggests that topiramate, at pharmacologically relevant concentrations, blocks voltage-dependent sodium channels, augments the activity of the neurotransmitter gamma-aminobutyrate at some subtypes of the GABA-A receptor, antagonizes the AMPA/kainate subtype of the glutamate receptor, and inhibits the carbonic anhydrase enzyme, particularly isozymes II and IV.

12.2 Pharmacodynamics

Topiramate has anticonvulsant activity in rat and mouse maximal electroshock seizure (MES) tests. Topiramate is only weakly effective in blocking clonic seizures induced by the GABA-A receptor antagonist, pentylenetetrazole. Topiramate is also effective in rodent models of epilepsy, which include tonic and absence-like seizures in the spontaneous epileptic rat (SER) and tonic and clonic seizures induced in rats by kindling of the amygdala or by global ischemia.

Changes (increases and decreases) from baseline in vital signs (systolic blood pressure-SBP, diastolic blood pressure-DBP, pulse) occurred more frequently in pediatric patients (6 to 17 years) treated with various daily doses of topiramate (50 mg, 100 mg, 200 mg, 2 to 3 mg/kg) than in patients treated with placebo in controlled trials for the preventive treatment of migraine. The most notable changes were SBP < 90 mm Hg, DBP < 50 mm Hg, SBP or DBP increases or decreases ≥ 20 mm Hg, and pulse increases or decreases ≥ 30 beats per minute. These changes were often dose-related, and were most frequently associated with the greatest treatment difference at the 200 mg dose level. Systematic collection of orthostatic vital signs has not been conducted. The clinical significance of these various changes in vital signs has not been clearly established.

12.3 Pharmacokinetics

Absorption and Distribution

Linear pharmacokinetics of topiramate from TROKENDI XR®were observed following a single oral dose over the range of 50 mg to 200 mg. At 25 mg, the pharmacokinetics of TROKENDI XR®is nonlinear possibly due to the binding of topiramate to carbonic anhydrase in red blood cells.

The peak plasma concentrations (Cmax) of topiramate occurred at approximately 24 hours following a single 200 mg oral dose of TROKENDI XR®. At steady-state, the (AUC0-24, Cmax, and Cmin) of topiramate from TROKENDI XR®administered once-daily and the immediate-release tablet administered twice-daily were shown to be bioequivalent. Fluctuation of topiramate plasma concentrations at steady-state for TROKENDI XR®administered once-daily was approximately 26% and 42% in healthy subjects and in epileptic patients, respectively, compared to approximately 40% and 51%, respectively, for immediate-release topiramate [see Clinical Pharmacology (12.6)] .

Compared to the fasted state, high-fat meal increased the Cmaxof topiramate by 37% and shortened the Tmaxto approximately 8 hours following a single dose of TROKENDI XR®, while having no effect on the AUC. Modeling of the observed single dose fed data with simulation to steady state showed that the effect on Cmaxis significantly reduced following repeat administrations. TROKENDI XR®can be taken without regard to meals.

Topiramate is 15% to 41% bound to human plasma proteins over the blood concentration range of 0.5 mcg/mL to 250 mcg/mL. The fraction bound decreased as blood concentration increased.

Carbamazepine and phenytoin do not alter the binding of immediate-release topiramate. Sodium valproate, at 500 mcg/mL (a concentration 5 to 10 times higher than considered therapeutic for valproate) decreased the protein binding of immediate-release topiramate from 23% to 13%. Immediate-release topiramate does not influence the binding of sodium valproate.

Metabolism and Excretion

Topiramate is not extensively metabolized and is primarily eliminated unchanged in the urine (approximately 70% of an administered dose). Six metabolites have been identified in humans, none of which constitutes more than 5% of an administered dose. The metabolites are formed via hydroxylation, hydrolysis, and glucuronidation. There is evidence of renal tubular reabsorption of topiramate. In rats, given probenecid to inhibit tubular reabsorption, along with topiramate, a significant increase in renal clearance of topiramate was observed. This interaction has not been evaluated in humans. Overall, oral plasma clearance (CL/F) is approximately 20 mL/min to 30 mL/min in adults following oral administration. The mean elimination half-life of topiramate was approximately 31 hours following repeat administration of TROKENDI XR®.

Specific Populations

Renal Impairment

The clearance of topiramate was reduced by 42% in subjects with moderate renal impairment (creatinine clearance 30 to 69 mL/min/1.73m^2) and by 54% in subjects with severe renal impairment (creatinine clearance less than 30 mL/min/1.73m^2) compared to subjects with normal renal function (creatinine clearance greater than 70 mL/min/1.73m^2) [see Dosage and Administration (2.5)] .

Hemodialysis

Topiramate is cleared by hemodialysis. Using a high-efficiency, counterflow, single pass-dialysate hemodialysis procedure, topiramate dialysis clearance was 120 mL/min with blood flow through the dialyzer at 400 mL/min. This high clearance (compared to 20 mL/min to 30 mL/min total oral clearance in healthy adults) will remove a clinically significant amount of topiramate from the patient over the hemodialysis treatment period [see Dosage and Administration (2.6)and Use in Specific Populations (8.7)] .

Hepatic Impairment

Plasma clearance of topiramate decreased a mean of 26% in patients with moderate to severe hepatic impairment.

Age, Gender, and Race

The pharmacokinetics of topiramate in elderly subjects (65 to 85 years of age, N=16) were evaluated in a controlled clinical study. The elderly subject population had reduced renal function (creatinine clearance [-20%]) compared to young adults. Following a single oral 100 mg dose, maximum plasma concentration for elderly and young adults was achieved at approximately 1 to 2 hours. Reflecting the primary renal elimination of topiramate, topiramate plasma and renal clearance were reduced 21% and 19%, respectively, in elderly subjects, compared to young adults. Similarly, topiramate half-life was longer (13%) in the elderly. Reduced topiramate clearance resulted in slightly higher maximum plasma concentration (23%) and AUC (25%) in elderly subjects than observed in young adults. Topiramate clearance is decreased in the elderly only to the extent that renal function is reduced [see Dosage and Administration (2.4)and Use in Specific Populations (8.5)].

In a study of 13 healthy elderly subjects and 18 healthy young adults who received TROKENDI XR®, 30% higher mean Cmaxand 44% higher AUC values were observed in elderly compared to young subjects. Elderly subjects exhibited shorter median Tmaxat 16 hours versus 24 hours in young subjects. The apparent elimination half-life was similar across age groups. As recommended for all patients, dosage adjustment is indicated in elderly patients with a creatinine clearance rate less than 70 mL/min/1.73 m^2) [see Dosage and Administration (2.5)and Use in Specific Populations (8.5)] .

Clearance of topiramate in adults was not affected by gender or race.

Pediatric Pharmacokinetics

Pharmacokinetics of immediate-release topiramate were evaluated in patients ages 2 to <16 years of age. Patients received either no or a combination of other antiepileptic drugs. A population pharmacokinetic model was developed on the basis of pharmacokinetic data from relevant topiramate clinical studies. This dataset contained data from 1217 subjects including 258 pediatric patients age 2 years to <16 years of age (95 pediatric patients less than 10 years of age). Pediatric patients on adjunctive treatment exhibited a higher oral clearance (L/h) of topiramate compared to patients on monotherapy, presumably because of increased clearance from concomitant enzyme-inducing antiepileptic drugs. In comparison, topiramate clearance per kg is greater in pediatric patients than in adults and in young pediatric patients (down to 2 years of age) than in older pediatric patients. Consequently, the plasma drug concentration for the same mg/kg/day dose would be lower in pediatric patients compared to adults and also in younger pediatric patients compared to older pediatric patients. Clearance was independent of dose.

As in adults, hepatic enzyme-inducing antiepileptic drugs decrease the steady state plasma concentrations of topiramate.

Pediatric Patients with Obesity

A population PK analysis of topiramate was conducted in 129 children <21 years of age with and without obesity to evaluate the potential impact of obesity on plasma topiramate exposures. Obesity was defined as BMI≥95 percentile for age and sex based on CDC-recommended BMI-for-age growth charts for males and females. Using the currently recommended dosing regimens, children with obesity are likely to have median values of average concentration at steady-state and trough concentration at steady-state that are up to 20% lower and 19% lower, respectively, compared to children without obesity. Dosage adjustment according to obesity status is not necessary.

Drug-Drug Interaction Studies

In vitrostudies indicate that topiramate does not inhibit CYP1A2, CYP2A6, CYP2B6, CYP2C9, CYP2D6, CYP2E1, and CYP3A4/5 isozymes. In vitrostudies indicate that immediate-release topiramate is a mild inhibitor of CYP2C19 and a mild inducer of CYP3A4. The same drug interactions can be expected with the use of TROKENDI XR®.

Antiepileptic Drugs

Potential interactions between immediate-release topiramate and standard AEDs were assessed in controlled clinical pharmacokinetic studies in patients with epilepsy. The effects of these interactions on mean plasma AUCs are summarized in Table 9. Interaction of TROKENDI XR®and standard AEDs is not expected to differ from the experience with immediate-release topiramate products.

In Table 9, the second column (AED concentration) describes what happens to the concentration of the co-administered AED listed in the first column when topiramate is added. The third column (topiramate concentration) describes how the co-administration of a drug listed in the first column modifies the concentration of topiramate when compared to topiramate given alone.

Table 9: Summary of AED Interactions with Topiramate
AED Coadministered | AED Concentration | Topiramate Concentration
Phenytoin | NC or 25% increase [=Plasma concentration increased 25% in some patients, generally those on a twice a day dosing regimen of phenytoin] | 48% decrease
Carbamazepine (CBZ) | NC | 40% decrease
CBZ epoxide [=Is not administered but is an active metabolite of carbamazepine] | NC | NE
Valproic acid | 11% decrease | 14% decrease
Phenobarbital | NC | NE
Primidone | NC | NE
Lamotrigine | NC at TPM doses up to 400mg per day | 13% decrease
NC=Less than 10% change in plasma concentration
AED=Antiepileptic drug
NE=Not evaluated
TPM=topiramate

Oral Contraceptives

In a pharmacokinetic interaction study in healthy volunteers with a concomitantly administered combination oral contraceptive product containing 1 mg norethindrone (NET) plus 35 mcg ethinyl estradiol (EE), immediate-release topiramate, given in the absence of other medications at doses of 50 to 200 mg/day, was not associated with statistically significant changes in mean exposure (AUC) to either component of the oral contraceptive. In another study, exposure to EE was statistically significantly decreased at doses of 200, 400, and 800 mg per day (18%, 21%, and 30%, respectively) when given as adjunctive therapy in patients taking valproic acid. In both studies, topiramate (50 mg per day to 800 mg per day) did not significantly affect exposure to NET, and there was no significant dose-dependent change in EE exposure for doses of 50 to 200 mg/day. The clinical significance of the changes observed is not known [see Drug Interactions (7.5)] .

Digoxin

In a single-dose study, serum digoxin AUC was decreased by 12% with concomitant topiramate administration. The clinical relevance of this observation has not been established.

Hydrochlorothiazide

A drug interaction study conducted in healthy volunteers evaluated the steady-state pharmacokinetics of hydrochlorothiazide (HCTZ) (25 mg every 24 hours) and topiramate (96 mg every 12 hours) when administered alone and concomitantly. The results of this study indicate that topiramate Cmaxincreased by 27% and AUC increased by 29% when HCTZ was added to topiramate. The clinical significance of this change is unknown. The steady-state pharmacokinetics of HCTZ were not significantly influenced by the concomitant administration of topiramate. Clinical laboratory results indicated decreases in serum potassium after topiramate or HCTZ administration, which were greater when HCTZ and topiramate were administered in combination [see Drug Interactions (7.6)].

Metformin

A drug interaction study conducted in healthy volunteers evaluated the steady-state pharmacokinetics of metformin (500 mg every 12 hours) and topiramate in plasma when metformin was given alone and when metformin and topiramate (100 mg every 12 hours) were given simultaneously. The results of this study indicated that the mean metformin Cmaxand AUC0-12hincreased by 17% and 25%, respectively, when topiramate was added. Topiramate did not affect metformin Tmax. The clinical significance of the effect of topiramate on metformin pharmacokinetics is not known. Oral plasma clearance of topiramate appears to be reduced when administered with metformin. The clinical significance of the effect of metformin on topiramate or TROKENDI XR®pharmacokinetics is unclear.

Pioglitazone

A drug interaction study conducted in healthy volunteers evaluated the steady-state pharmacokinetics of topiramate and pioglitazone when administered alone and concomitantly. A 15% decrease in the AUCτ,ssof pioglitazone with no alteration in Cmax,sswas observed. This finding was not statistically significant. In addition, a 13% and 16% decrease in Cmax,ssand AUCτ,ssrespectively, of the active hydroxy-metabolite was noted as well as a 60% decrease in Cmax,ssand AUCτ,ssof the active keto-metabolite. The clinical significance of these findings is not known [see Drug Interactions (7.7)].

Glyburide

A drug interaction study conducted in patients with type 2 diabetes evaluated the steady-state pharmacokinetics of glyburide (5 mg per day) alone and concomitantly with topiramate (150 mg per day). There was a 22% decrease in Cmaxand 25% reduction in AUC24for glyburide during topiramate administration. Systemic exposure (AUC) of the active metabolites, 4- trans-hydroxy glyburide (M1) and 3- cis-hydroxyglyburide (M2), was also reduced by 13% and 15%, reduced Cmaxby 18% and 25%, respectively. The steady-state pharmacokinetics of topiramate were unaffected by concomitant administration of glyburide.

Lithium

In patients, the pharmacokinetics of lithium were unaffected during treatment with topiramate at doses of 200 mg per day; however, there was an observed increase in systemic exposure of lithium (27% for Cmaxand 26% for AUC) following topiramate doses up to 600 mg per day [see Drug Interactions (7.8)].

Haloperidol

The pharmacokinetics of a single dose of haloperidol (5 mg) were not affected following multiple dosing of topiramate (100 mg every 12 hr) in 13 healthy adults (6 males, 7 females).

Amitriptyline

There was a 12% increase in AUC and Cmaxfor amitriptyline (25 mg per day) in 18 healthy subjects (9 males, 9 females) receiving 200 mg per day of immediate-release topiramate [see Drug Interactions (7.9)].

Sumatriptan

Multiple dosing of topiramate (100 mg every 12 hours) in 24 healthy volunteers (14 males, 10 females) did not affect the pharmacokinetics of single-dose sumatriptan either orally (100 mg) or subcutaneously (6 mg).

Risperidone

When administered concomitantly with topiramate at escalating doses of 100, 250, and 400 mg per day, there was a reduction in risperidone systemic exposure (16% and 33% for steady-state AUC at the 250 and 400 mg per day doses of topiramate). No alterations of 9-hydroxyrisperidone levels were observed. Coadministration of topiramate 400 mg per day with risperidone resulted in a 14% increase in Cmaxand a 12% increase in AUC12of topiramate. There were no clinically significant changes in the systemic exposure of risperidone plus 9-hydroxyrisperidone or of topiramate; therefore, this interaction is not likely to be of clinical significance.

Propranolol

Multiple dosing of topiramate (200 mg per day) in 34 healthy volunteers (17 males, 17 females) did not affect the pharmacokinetics of propranolol following daily 160 mg doses. Propranolol doses of 160 mg per day in 39 volunteers (27 males, 12 females) had no effect on the exposure to topiramate at a dose of 200 mg/day of topiramate.

Dihydroergotamine

Multiple dosing of topiramate (200 mg/day) in 24 healthy volunteers (12 males, 12 females) did not affect the pharmacokinetics of a 1 mg subcutaneous dose of dihydroergotamine. Similarly, a 1 mg subcutaneous dose of dihydroergotamine did not affect the pharmacokinetics of a 200 mg/day dose of topiramate in the same study.

Diltiazem

Co-administration of diltiazem (240 mg Cardizem CD®) with topiramate (150 mg/day) resulted in a 10% decrease in Cmaxand 25% decrease in diltiazem AUC, 27% decrease in Cmaxand 18% decrease in des-acetyl diltiazem AUC, and no effect on N-desmethyl diltiazem. Co-administration of topiramate with diltiazem resulted in a 16% increase in Cmaxand a 19% increase in AUC12of topiramate.

Venlafaxine

Multiple dosing of topiramate (150 mg/day) in healthy volunteers did not affect the pharmacokinetics of venlafaxine or O-desmethyl venlafaxine. Multiple dosing of venlafaxine (150 mg) did not affect the pharmacokinetics of topiramate.

12.6 Relative Bioavailability of TROKENDI XR®Compared to Immediate-Release Topiramate

Study in Healthy Normal Volunteers

TROKENDI XR®taken once a day provides steady state plasma levels comparable to immediate-release topiramate taken every 12 hours, when administered at the same total 200-mg daily dose. In a crossover study, 33 healthy subjects were titrated to a 200-mg dose of either TROKENDI XR®or immediate-release topiramate and were maintained at 200 mg per day for 10 days.

The 90% CI for the ratios of AUC0-24, Cmaxand Cmin, as well as partial AUC (the area under the concentration-time curve from time 0 to time p (post dose) for multiple time points were within the 80 to 125% bioequivalence limits, indicating no clinically significant difference between the two formulations. In addition, the 90% CI for the ratios of topiramate plasma concentration at each of multiple time points over 24 hours for the two formulations were within the 80 to 125% bioequivalence limits, except for the initial time points before 1.5 hours post-dose.

Study in Patients with Epilepsy

In a study in epilepsy patients treated with immediate-release topiramate alone or in combination with either enzyme-inducing or neutral AEDs who were switched to an equivalent daily dose of TROKENDI XR®, there was a 10% decrease in AUC0-24, Cmax, and Cminon the first day after the switch in all patients. At steady state, AUC0-24and Cmaxwere comparable to immediate-release topiramate in all patients. While patients treated with TROKENDI XR®alone or in combination with neutral AEDs showed comparable Cminat steady state, patients treated with enzyme-inducers showed a 10% decrease in Cmin. This difference is likely not clinically significant and probably due to the small number of patients on enzyme-inducers.

13 NONCLINICAL TOXICOLOGY

13.1 Carcinogenesis, Mutagenesis, and Impairment of Fertility

Carcinogenesis

An increase in urinary bladder tumors was observed in mice given topiramate (0, 20, 75, and 300 mg/kg/day) in the diet for 21 months. An increase in the incidence of bladder tumors in males and females receiving 300 mg/kg was primarily due to the increased occurrence of a smooth muscle tumor considered histomorphologically unique to mice. The higher of the doses not associated with an increase in tumors (75 mg/kg/day) is equivalent to the maximum recommended human dose (MRHD) for epilepsy and approximately 4 times the MRHD for migraine (100 mg) on a mg/m^2basis. The relevance of this finding to human carcinogenic risk is uncertain. No evidence of carcinogenicity was seen in rats following oral administration of topiramate for 2 years at doses up to 120 mg/kg/day (approximately 3 times the MRHD for epilepsy and 12 times the MRHD for migraine on a mg/m^2basis).

Mutagenesis

Topiramate did not demonstrate genotoxic potential when tested in a battery of in vitroand in vivoassays. Topiramate was not mutagenic in the Ames test or the in vitromouse lymphoma assay; it did not increase unscheduled DNA synthesis in rat hepatocytes in vitro;and it did not increase chromosomal aberrations in human lymphocytes in vitroor in rat bone marrow in vivo.

Impairment of Fertility

No adverse effects on male or female fertility were observed in rats administered oral doses of up to 100 mg/kg/day (2.5 times the MRHD for epilepsy and 10 times the MRHD for migraine on a mg/m^2basis) prior to and during mating and early pregnancy.

14 CLINICAL STUDIES

14.1 Bridging Study to Demonstrate Pharmacokinetic Equivalence between Extended-Release and Immediate-Release Topiramate Formulations

The basis for approval of the extended-release formulation (TROKENDI XR®) included the studies described below using an immediate-release formulation and the demonstration of the pharmacokinetic equivalence of TROKENDI XR®to immediate-release topiramate through the analysis of concentrations and cumulative AUCs at multiple time points [see Clinical Pharmacology (12.6)].

The clinical studies described in the following sections were conducted using immediate-release topiramate.

14.2 Monotherapy Epilepsy

Patients With Partial-Onset or Primary Generalized Tonic-Clonic Seizures

Adults and Pediatric Patients 10 Years of Age and Older

The effectiveness of topiramate as initial monotherapy in adults and pediatric patients 10 years of age and older with partial onset or primary generalized tonic-clonic seizures was established in a multicenter, randomized, double-blind, dose-controlled, parallel-group trial (Study 1).

Study 1 was conducted in 487 patients diagnosed with epilepsy (6 to 83 years of age) who had 1 or 2 well-documented seizures during the 3-month retrospective baseline phase who then entered the study and received topiramate 25 mg per day for 7 days in an open-label fashion. Forty-nine percent of subjects had no prior AED treatment and 17% had a diagnosis of epilepsy for greater than 24 months. Any AED therapy used for temporary or emergency purposes was discontinued prior to randomization. In the double-blind phase, 470 patients were randomized to titrate up to 50 mg/day or 400 mg/day of topiramate. If the target dose could not be achieved, patients were maintained on the maximum tolerated dose. Fifty-eight percent of patients achieved the maximal dose of 400 mg/day for >2 weeks, and patients who did not tolerate 150 mg/day were discontinued.

The primary efficacy assessment was a between-group comparison of time to first seizure during the double-blind phase. Comparison of the Kaplan-Meier survival curves of time to first seizure favored the topiramate 400 mg/day group over the topiramate 50 mg/day group (Figure 1). The treatment effects with respect to time to first seizure were consistent across various patient subgroups defined by age, sex, geographic region, baseline body weight, baseline seizure type, time since diagnosis, and baseline AED use.

Figure 1: Kaplan-Meier Estimates of Cumulative Rates for Time to First Seizure in Study 1

Pediatric Patients 6 to 9 Years of Age

The conclusion that topiramate is effective as initial monotherapy in pediatric patients 6 to 9 years of age with partial-onset or primary generalized tonic-clonic seizures was based on a pharmacometric bridging approach using data from the controlled epilepsy trials conducted with immediate-release topiramate described in labeling. The approach consisted of first showing a similar exposure response relationship between pediatric patients down to 2 years of age and adults when immediate-release topiramate was given as adjunctive therapy [see Use in Specific Populations (8.4)] . Similarity of exposure-response was demonstrated in pediatric patients 6 to less than 16 years of age and adults when topiramate was given as initial monotherapy. Specific dosing in pediatric patients 6 to 9 years of age was derived from simulations utilizing plasma exposure ranges observed in pediatric and adult patients treated with immediate-release topiramate initial monotherapy [see Dosage and Administration (2.1)] .

14.3 Adjunctive Therapy Epilepsy

Adult Patients With Partial-Onset Seizures

The effectiveness of topiramate as an adjunctive treatment for adults with partial-onset seizures was established in six multicenter, randomized, double-blind, placebo-controlled trials (Studies 2, 3, 4, 5, 6, and 7), two comparing several dosages of topiramate and placebo and four comparing a single dosage with placebo, in patients with a history of partial onset seizures, with or without secondarily generalized seizures.

Patients in these studies were permitted a maximum of two antiepileptic drugs (AEDs) in addition to topiramate tablets or placebo. In each study, patients were stabilized on optimum dosages of their concomitant AEDs during baseline phase lasting between 4 and 12 weeks. Patients who experienced a pre-specified minimum number of partial-onset seizures, with or without secondary generalization, during the baseline phase (12 seizures for 12-week baseline, 8 for 8-week baseline or 3 for 4-week baseline) were randomly assigned to placebo or a specified dose of topiramate tablets in addition to their other AEDs.

Following randomization, patients began the double-blind phase of treatment. In five of the six studies, patients received active drug beginning at 100 mg per day; the dose was then increased by 100 mg or 200 mg/day increments weekly or every other week until the assigned dose was reached, unless intolerance prevented increases. In Study 7, the 25 or 50 mg/day initial doses of topiramate were followed by respective weekly increments of 25 or 50 mg/day until the target dose of 200 mg/day was reached. After titration, patients entered a 4, 8 or 12-week stabilization period. The numbers of patients randomized to each dose, and the actual mean and median doses in the stabilization period are shown in Table 10.

Pediatric Patients 6 to 16 Years of Age With Partial-Onset Seizures

The effectiveness of topiramate as an adjunctive treatment for pediatric patients 6 to 16 years of age with partial-onset seizures was established in a multicenter, randomized, double-blind, placebo-controlled trial (Study 8), comparing topiramate and placebo in patients with a history of partial-onset seizures, with or without secondarily generalized seizures.

Patients in Study 8 were permitted a maximum of two antiepileptic drugs (AEDs) in addition to topiramate tablets or placebo. In Study 8, patients were stabilized on optimum dosages of their concomitant AEDs during an 8-week baseline phase. Patients who experienced at least six partial onset seizures, with or without secondarily generalized seizures, during the baseline phase were randomly assigned to placebo or topiramate in addition to their other AEDs.

Following randomization, patients began the double-blind phase of treatment. Patients received active drug beginning at 25 or 50 mg/day; the dose was then increased by 25 mg to 150 mg/day increments every other week until the assigned dosage of 125, 175, 225 or 400 mg/day based on patients' weight to approximate a dosage of 6 mg/kg/day per day was reached, unless intolerance prevented increases. After titration, patients entered an 8-week stabilization period.

Patients With Primary Generalized Tonic-Clonic Seizures

The effectiveness of topiramate as an adjunctive treatment for primary generalized tonic-clonic seizures in patients 6 years of age and older was established in a multicenter, randomized, double-blind, placebo-controlled trial (Study 9), comparing a single dosage of topiramate and placebo (see Table 11).

Patients in Study 9 were permitted a maximum of two antiepileptic drugs (AEDs) in addition to topiramate or placebo. Patients were stabilized on optimum dosages of their concomitant AEDs during an 8-week baseline phase. Patients who experienced at least three primary generalized tonic-clonic seizures during the baseline phase were randomly assigned to placebo or topiramate in addition to their other AEDs.

Following randomization, patients began the double-blind phase of treatment. Patients received active drug beginning at 50 mg/day for four weeks; the dose was then increased by 50 mg to 150 mg/day increments every other week until the assigned dose of 175, 225 or 400 mg/day based on patients' body weight to approximate a dosage of 6 mg/kg/day was reached, unless intolerance prevented increases. After titration, patients entered a 12-week stabilization period.

Patients With Lennox-Gastaut Syndrome

The effectiveness of topiramate as an adjunctive treatment for seizures associated with Lennox-Gastaut syndrome in patients 6 years of age and older was established in a multicenter, randomized, double-blind, placebo-controlled trial (Study 10), comparing a single dosage of topiramate with placebo (see Table 11).

Patients in Study 10 were permitted a maximum of two antiepileptic drugs (AEDs) in addition to topiramate or placebo. Patients who were experiencing at least 60 seizures per month before study entry were stabilized on optimum dosages of their concomitant AEDs during a 4 week baseline phase. Following baseline, patients were randomly assigned to placebo or topiramate in addition to their other AEDs. Active drug was titrated beginning at 1 mg/kg/day for a week; the dose was then increased to 3 mg/kg/day for one week then to 6 mg/kg/day. After titration, patients entered an 8-week stabilization period. The primary measures of effectiveness were the percent reduction in drop attacks and a parental global rating of seizure severity.

Table 10: Immediate Release Topiramate Dose Summary During the Stabilization Periods of Each of Six Double-Blind, Placebo-Controlled, Adjunctive Trials in Adults With Partial-Onset Seizures [Dose-response studies were not conducted for other indications or pediatric partial-onset seizures]
Target Topiramate Dosage (mg per day)
Study | Stabilization Dose | Placebo [Placebo dosages are given as the number of tablets. Placebo target dosages were as follows: Study 4 (4 tablets/day); Studies 2 and 5 (6 tablets/day); Studies 6 and 7 (8 tablets/day); Study 3 (10 tablets/day)] | 200 | 400 | 600 | 800 | 1,000
2 | N | 42 | 42 | 40 | 41 | -- | --
2 | Mean Dose | 5.9 | 200 | 390 | 556 | -- | --
2 | Median Dose | 6.0 | 200 | 400 | 600 | -- | --
3 | N | 44 | -- | -- | 40 | 45 | 40
3 | Mean Dose | 9.7 | -- | -- | 544 | 739 | 796
3 | Median Dose | 10.0 | -- | -- | 600 | 800 | 1,000
4 | N | 23 | -- | 19 | -- | -- | --
4 | Mean Dose | 3.8 | -- | 395 | -- | -- | --
4 | Median Dose | 4.0 | -- | 400 | -- | -- | --
5 | N | 30 | -- | -- | 28 | -- | --
5 | Mean Dose | 5.7 | -- | -- | 522 | -- | --
5 | Median Dose | 6.0 | -- | -- | 600 | -- | --
6 | N | 28 | -- | -- | -- | 25 | --
6 | Mean Dose | 8.0 | -- | -- | -- | 568 | --
6 | Median Dose | 8.0 | -- | -- | -- | 600 | --
7 | N | 90 | 157 | -- | -- | -- | --
7 | Mean Dose | 8 | 200 | -- | -- | -- | --
7 | Median Dose | 8 | 200 | -- | -- | -- | --

In all adjunctive topiramate trials, the reduction in seizure rate from baseline during the entire double-blind phase was measured. The median percent reductions in seizure rates and the responder rates (fraction of patients with at least a 50% reduction) by treatment group for each study are shown below in Table 11. As described above, a global improvement in seizure severity was also assessed in the Lennox-Gastaut trial.

Table 11: Efficacy Results in Double-Blind, Placebo-Controlled, Adjunctive Epilepsy Trials
Target Topiramate Dosage (mg per day)
Study # | # | Placebo | 200 | 400 | 600 | 800 | 1,000 | ≈6mg/kg/day [For Studies 8 and 9, specified target dosages (<9.3 mg/kg/day) were assigned based on subject's weight to approximate a dosage of 6mg/kg per day; these dosages corresponded to mg/day dosages of 125, 175, 225, and 400 mg/day]
Partial Onset Seizures Studies in Adults
2 | N | 45 | 45 | 45 | 46 | -- | -- | --
2 | Median % Reduction | 12 | 27 [p=0.080;] | 48 [p ≤ 0.010;] | 45 [p ≤ 0.001;] | -- | -- | --
2 | % Responders | 18 | 24 | 44 [p ≤ 0.050;] | 46 | -- | -- | --
3 | N | 47 | -- | -- | 48 | 48 | 47 | --
3 | Median % Reduction | 2 | -- | -- | 41 | 41 | 36
3 | % Responders | 9 | -- | -- | 40 | 41 | 36
4 | N | 24 | -- | 23 | -- | -- | -- | --
4 | Median % Reduction | 1 | -- | 41 [p=0.065;] | -- | -- | -- | --
4 | % Responders | 8 | -- | 35 | -- | -- | -- | --
5 | N | 30 | -- | -- | 30 | -- | -- | --
5 | Median % Reduction | -12 | -- | -- | 46 [p ≤0.005;] | -- | -- | --
5 | % Responders | 10 | -- | -- | 47 | -- | -- | --
6 | N | 28 | -- | -- | -- | 28 | -- | --
6 | Median % Reduction | -21 | -- | -- | -- | 24 | -- | --
6 | % Responders | 0 | -- | -- | -- | 43 | -- | --
7 | N | 91 | 168 | -- | -- | -- | -- | --
7 | Median % Reduction | 20 | 44 | -- | -- | -- | -- | --
7 | % Responders | 24 | 45
Partial Onset Seizures Studies in Pediatric Patients [Studies included pediatric patients 2 years of age and older, an age group for which TROKENDI XR is not indicated [see Indications and Usage (1.2) and Use in Specific Populations (8.4)]]
8 | N | 45 | -- | -- | -- | -- | -- | 41
8 | Median % Reduction | 11 | -- | -- | -- | -- | -- | 33
8 | % Responders | 20 | -- | -- | -- | -- | -- | 39
Primary Generalized Tonic-Clonic [Median % reduction and % responders are reported for PGTC seizures;] ,
9 | N | 40 | -- | -- | -- | -- | -- | 39
9 | Median % Reduction | 9 | -- | -- | -- | -- | -- | 57
9 | % Responders | 20 | -- | -- | -- | -- | -- | 56
Lennox-Gastaut Syndrome [Median % reduction and % responders for drop attacks, i.e., tonic or atonic seizures] ,
10 | N | 49 | -- | -- | -- | -- | -- | 46
10 | Median % Reduction | -5 | -- | -- | -- | -- | -- | 15
10 | % Responders | 14 |  |  |  |  |  | 28 [p=0.071;]
10 | Improvement in Seizure Severity [Percentage of subjects who were minimally, much, or very much improved from baseline.] | 28 |  |  |  |  |  | 52
Comparisons with placebo:

Subset analyses of the antiepileptic efficacy of topiramate tablets in these studies showed no differences as a function of gender, race, age, baseline seizure rate, or concomitant AED.

In clinical trials for epilepsy, daily dosages were decreased in weekly intervals by 50 mg per day to 100 mg per day in adults and over a 2- to 8-week period in pediatric patients; transition was permitted to a new antiepileptic regimen when clinically indicated.

14.4 Preventive Treatment of Migraine

Adult Patients

The results of 2 multicenter, randomized, double-blind, placebo-controlled, parallel-group clinical trials conducted in US (Study 11) or the US and Canada (Study 12) established the effectiveness of immediate-release topiramate in the preventive treatment of migraine. The design of both trials was identical, enrolling patients with a history of migraine with or without aura, for at least 6 months, according to the International Headache Society (IHS) diagnostic criteria. Patients with a history of cluster headaches or basilar, opthalmoplegic, hemiplegic, or transformed migraine headaches were excluded from the trials. Patients were required to have completed up to a 2-week washout of any prior migraine preventative medications before starting the baseline phase.

Patients who experienced 3 to 12 migraine headaches over the 4 weeks in the baseline phase were randomized to either immediate-release topiramate 50 mg/day, 100 mg/day, 200 mg/day (twice the recommended daily dosage for migraine prophylaxis) or placebo, and treated for a total of 26 weeks (8-week titration period and 18-week maintenance period.). Treatment was initiated at 25 mg/day for one week, and then the daily dosage was increased by 25 mg increments each week until reaching the assigned target dose or maximum tolerated dose (administered twice daily).

Effectiveness of treatment was assessed by the reduction in migraine headache frequency, as measured by the change in 4-week migraine rate (according to migraines classified by IHS criteria) from the baseline phase to double-blind treatment period in each immediate-release topiramate treatment group compared to placebo in the Intent-To-Treat (ITT) population.

In Study 11, a total of 469 patients (416 females, 53 males) ranging in age from 13 to 70 years, were randomized and provided efficacy data. Two hundred sixty-five patients completed the entire 26-week double-blind phase. The median average daily dosages were 48 mg/day, 88 mg/day, and 132 mg/day in the target dose groups of topiramate 50, 100 and 200 mg/day, respectively.

The mean migraine headache frequency rate at baseline was approximately 5.5 migraine headaches per 28 days and was similar across treatment groups. The change in the mean 4-week migraine headache frequency from baseline to the double-blind phase was -1.3, -2.1, and -2.2 in the immediate-release topiramate 50, 100, and 200 mg/day groups, respectively, versus -0.8 in the placebo group (see Figure 2). The treatment differences between the immediate release topiramate 100 and 200 mg/day groups versus placebo were similar and statistically significant (p < 0.001 for both comparisons).

In Study 12, a total of 468 patients (406 females, 62 males) ranging in age from 12 to 65 years, were randomized and provided efficacy data. Two hundred fifty-five patients completed the entire 26-week double-blind phase. The median average daily dosages were 47 mg/day, 86 mg/day, and 150 mg/day in the target dose groups of immediate-release topiramate 50, 100, and 200 mg/day, respectively.

The mean migraine headache frequency rate at baseline was approximately 5.5 migraine headaches per 28 days and was similar across treatment groups. The change in the mean 4-week migraine headache period frequency from baseline to the double-blind phase was -1.4, -2.1, and -2.4 in the immediate-release topiramate 50, 100, and 200 mg/day groups, respectively, versus -1.1 in the placebo group (see Figure 2). The differences between the immediate-release topiramate 100 and 200 mg per day groups versus placebo were similar and statistically significant (p = 0.008 and p < 0.001, respectively).

In both studies there were no apparent differences in treatment effect within age or gender subgroups. Because most patients were Caucasian, there were insufficient numbers of patients from different races to make a meaningful comparison of race.

For patients withdrawing from immediate-release topiramate, daily dosages were decreased in weekly intervals by 25 to 50 mg/day.

Figure 2: Reduction in 4-Week Migraine Headache Frequency (Studies 11 and 12 for Adults and Adolescents)

Pediatric Patients 12 to 17 Years of Age

The effectiveness of immediate-release topiramate for the preventive treatment of migraine in pediatric patients 12 to 17 years of age was established in a multicenter, randomized, double-blind, parallel-group trial (Study 13). The study enrolled 103 patients (40 male, 63 female) 12 to 17 years of age with episodic migraine headaches with or without aura. Patient selection was based on IHS criteria for migraines (using proposed revisions to the 1988 IHS pediatric migraine criteria [IHS-R criteria]).

Patients who experienced 3 to 12 migraine attacks (according to migraines classified by patient reported diaries) and ≤14 headache days (migraine and non-migraine) during the 4-week prospective baseline period were randomized to either immediate-release topiramate 50 mg/day, 100 mg/day, or placebo and treated for a total of 16 weeks (4-week titration period followed by a 12 week maintenance period). Treatment was initiated at 25 mg/day for one week, and then the daily dosage was increased by 25 mg increments each week until reaching the assigned target dose or maximum tolerated dose (administered twice daily). Approximately 80% or more patients in each treatment group completed the study. The median average daily dosages were 45 and 79 mg/day in the target dose groups of immediate-release topiramate 50 and 100 mg/day, respectively.

Effectiveness of treatment was assessed by comparing each immediate-release topiramate treatment group to placebo (ITT population) for the percent reduction from baseline to the last 12 weeks of the double-blind phase in the monthly migraine attack rate (primary endpoint). The percent reduction from baseline to the last 12 weeks of the double-blind phase in average monthly migraine attack rate is shown in Table 12. The 100 mg immediate-release topiramate dose produced a statistically significant treatment difference relative to placebo of 28% reduction from baseline in the monthly migraine attack rate.

The mean reduction from baseline to the last 12 weeks of the double-blind phase in average monthly attack rate, a key secondary efficacy endpoint in Study 13 (and the primary efficacy endpoint in Studies 11 and 12, of adults) was 3.0 for 100 mg immediate-release topiramate dose and 1.7 for placebo. This 1.3 treatment difference in mean reduction from baseline of monthly migraine rate was statistically significant (p=0.0087).

Table 12: Percent Reduction from Baseline to the Last 12 Weeks of Double- Blind Phase in Average Monthly Attack Rate: Study 13 (Intent-to-Treat Analysis Set)
Category | Placebo (N=33) | Immediate-Release Topiramate 50 mg/day (N=35) | Immediate-Release Topiramate 100 mg/day (N=35)
Baseline
Median | 3.6 | 4.0 | 4.0
Last 12 Weeks of Double-Blind Phase
Median | 2.3 | 2.3 | 1.0
Percent Reduction (%)
Median | 44.4 | 44.6 | 72.2
P-value versus Placebo [P-values (two-sided) for comparisons relative to placebo are generated by applying an ANCOVA model on ranks that includes subject's stratified age at baseline, treatment group, and analysis center as factors and monthly migraine attack rate during baseline period as a covariate.] , [P-values for the dose groups are the adjusted p-value according to the Hochberg multiple comparison procedure.] |  | 0.7975 | 0.0164 [Indicates p-value is <0.05 (two-sided).]

16 HOW SUPPLIED/STORAGE AND HANDLING

16.1 How Supplied

TROKENDI XR®(topiramate) extended-release capsules are available in the following strengths and colors:

25 mg (light green opaque body/yellow opaque cap with black print "SPN" and "25"):

- bottles of 7 count (NDC-17772-101-70), 30 count (NDC-17772-101-30) and 100 count (NDC-17772-101-01)
- blister packages of 30-count (NDC-17772-101-15)

50 mg (light green opaque body/orange opaque cap with black print "SPN" and "50"):

- bottles of 7 count (NDC-17772-102-70), 30 count (NDC-17772-102-30) and 100 count (NDC-17772-102-01)
- blister packages of 30-count (NDC-17772-102-15)

100 mg (green opaque body/blue opaque cap with black print "SPN" and "100"):

- bottles of 7 count (NDC-17772-103-70), 30 count (NDC-17772-103-30) and 100 count (NDC-17772-103-01)
- blister packages of 30-count (NDC-17772-103-15)

200 mg (pink opaque body/blue opaque cap with black print "SPN" and "200"):

- bottles of 7 count (NDC-17772-104-70), 30 count (NDC-17772-104-30) and 100 count (NDC-17772-104-01)
- blister packages of 30-count (NDC-17772-104-15)

16.2 Storage and Handling

TROKENDI XR®(topiramate) extended-release capsules should be stored in well closed containers at controlled room temperature [25°C (77°F); excursions 15°C-30°C (59°F-86°F)]. Protect from moisture and light.

17 PATIENT COUNSELING INFORMATION

Advise the patient to read the FDA-approved patient labeling (Medication Guide).

Administration Instructions

Counsel patients to swallow TROKENDI XR®capsules whole and intact. TROKENDI XR®should not be sprinkled on food, chewed, or crushed [see Dosage and Administration (2.7)].

Consumption of Alcohol

Advise patients to completely avoid consumption of alcohol at least 6 hours prior to and 6 hours after taking TROKENDI XR® [see Warnings and Precautions (5.5)] .

Eye Disorders

Advise patients taking TROKENDI XR®to seek immediate medical attention if they experience blurred vision, visual disturbances, or periorbital pain [see Warnings and Precautions (5.1, 5.2)] .

Oligohydrosis and Hyperthermia

Counsel patients that TROKENDI XR®, especially pediatric patients, can cause decreased sweating and increased body temperature, especially in hot weather, and they should seek medical attention if this is noticed [see Warnings and Precautions (5.3)] .

Metabolic Acidosis

Inform patients about the potentially significant risk for metabolic acidosis that may be asymptomatic and may be associated with adverse effects on kidneys (e.g., kidney stones, nephrocalcinosis), bones (e.g., osteoporosis, osteomalacia, and/or rickets in children), and growth (e.g., growth delay/retardation) in pediatric patients, and on the fetus [see Warnings and Precautions (5.4)] .

Suicidal Behavior and Ideation

Counsel patients, their caregivers, and families that AEDs, including TROKENDI XR®, may increase the risk of suicidal thoughts and behavior and they should be advised of the need to be alert for the emergence or worsening of the signs and symptoms of depression, any unusual changes in mood or behavior or the emergence of suicidal thoughts, behavior, or thoughts about self-harm. Behaviors of concern should be reported immediately to healthcare providers [see Warnings and Precautions (5.6)].

Interference With Cognitive and Motor Performance

Warn patients about the potential for somnolence, dizziness, confusion, difficulty concentrating, or visual effects and advise them not to drive or operate machinery until they have gained sufficient experience on TROKENDI XR®to gauge whether it adversely affects their mental performance, motor performance, and/or vision [see Warnings and Precautions (5.7)] .

Advise patients that even when taking TROKENDI XR®or other anticonvulsants, some patients with epilepsy will continue to have unpredictable seizures. Therefore, counsel all patients taking TROKENDI XR®for epilepsy to exercise appropriate caution when engaging in any activities where loss of consciousness could result in serious danger to themselves or those around them (including swimming, driving a car, climbing in high places, etc.). Some patients with refractory epilepsy will need to avoid such activities altogether. Physicians should discuss the appropriate level of caution with their patients, before patients with epilepsy engage in such activities.

Fetal Toxicity

Counsel pregnant women and women of childbearing potential that use of TROKENDI XR during pregnancy can cause fetal harm. TROKENDI increases the risk of major congenital malformations, including but not limited to cleft lip and/or cleft palate (oral clefts), which occur early in pregnancy before many women know they are pregnant. Also inform patients that infants exposed to topiramate monotherapy in uteromay be SGA [see Use in Specific Populations (8.1)] . There may also be risks to the fetus from chronic metabolic acidosis with use of TROKENDI XR during pregnancy [see Warnings and Precautions (5.4, 5.8)]. When appropriate, prescribers should counsel pregnant women and women of childbearing potential about alternative therapeutic options.

Advise women of childbearing potential who are not planning a pregnancy to use effective contraception while using topiramate, keeping in mind that there is a potential for decreased contraceptive efficacy when using estrogen-containing or progestin-only contraceptives with topiramate [see Warnings and Precautions (5.8)and Drug Interactions (7.5)] .

Encourage pregnant women using TROKENDI XR to enroll in the North American Antiepileptic Drug (NAAED) Pregnancy Registry. The registry is collecting information about the safety of antiepileptic drugs during pregnancy [see Use in Specific Populations (8.1)] .

Decrease in Bone Mineral Density

Inform the patient or caregiver that long-term treatment with TROKENDI XR can decrease bone formation and increase bone resorption in children [see Warnings and Precautions (5.10)].

Negative Effects on Growth (Height and Weight)

Discuss with the patient or caregiver that long-term TROKENDI XR treatment may attenuate growth as reflected by slower height increase and weight gain in pediatric patients [see Warnings and Precautions (5.11)].

Serious Skin Reactions

Inform patients about the signs of serious skin reactions. Instruct patients to immediately inform their healthcare provider at the first appearance of skin rash [see Warnings and Precautions (5.12)] .

Hyperammonemia and Encephalopathy

Warn patients about the possible development of hyperammonemia with or without encephalopathy. Although hyperammonemia may be asymptomatic, clinical symptoms of hyperammonemic encephalopathy often include acute alterations in level of consciousness and/or cognitive function with lethargy or vomiting. This hyperammonemia and encephalopathy can develop with topiramate treatment alone or with topiramate treatment with concomitant valproic acid (VPA). Patients should be instructed to contact their physician if they develop unexplained lethargy, vomiting, or changes in mental status [see Warnings and Precautions (5.13)] .

Kidney Stones

Instruct patients, particularly those with predisposing factors, to maintain an adequate fluid intake in order to minimize the risk of kidney stone formation [see Warnings and Precautions (5.14)] .

Hypothermia

Counsel patients that TROKENDI XR®can cause a reduction in body temperature, which can lead to alterations in mental status. If they note such changes, they should call their health care professional and measure their body temperature. Patients taking concomitant valproic acid should be specifically counseled on this potential adverse reaction [see Warnings and Precautions (5.15)] .

Manufactured by: Catalent Pharma Solutions, Winchester, Kentucky 40391

Manufactured for: Supernus Pharmaceuticals, Inc., Rockville, Maryland 20850

RA-TRO-V16

MEDICATION GUIDE
TROKENDI XR (tro-KEN-dee eks ahr)
(topiramate)
Extended-Release Capsules

What is the most important information I should know about Trokendi XR?
Take Trokendi XR®capsules whole. Do not sprinkle Trokendi XR®on food, or break, crush, dissolve, or chew Trokendi XR®capsules before swallowing. If you cannot swallow Trokendi XR®capsules whole, tell your healthcare provider. You may need a different medicine.
Do not drink alcohol within 6 hours prior to and 6 hours after Trokendi XR®administration.
Trokendi XR may cause eye problems.Serious eye problems include:

- any sudden decrease in vision with or without eye pain and redness,
- a blockage of fluid in the eye causing increased pressure in the eye (secondary angle closure glaucoma).
- These eye problems can lead to permanent loss of vision if not treated.
- You should call your healthcare provider right away if you have any new eye symptoms, including any new problems with your vision.

Trokendi XR may cause decreased sweating and increased body temperature (fever).People, especially children, should be watched for signs of decreased sweating and fever, especially in hot temperatures. Some people may need to be hospitalized for this condition. If a high fever, a fever that does not go away, or decreased sweating develops, call your healthcare provider right away.
Trokendi XR can increase the level of acid in your blood (metabolic acidosis).If left untreated, metabolic acidosis can cause brittle or soft bones (osteoporosis, osteomalacia, osteopenia), kidney stones, can slow the rate of growth in children, and may possibly harm your baby if you are pregnant. Metabolic acidosis can happen with or without symptoms. Sometimes people with metabolic acidosis will:

- feel tired
- not feel hungry (loss of appetite)
- feel changes in heartbeat
- have trouble thinking clearly

Your healthcare provider should do a blood test to measure the level of acid in your blood before and during your treatment with Trokendi XR. If you are pregnant, you should talk to your healthcare provider about whether you have metabolic acidosis.
Like other antiepileptic drugs, Trokendi XR may cause suicidal thoughts or actions in a very small number of people, about 1 in 500.
Call a healthcare provider right away if you have any of these symptoms, especially if they are new, worse, or worry you:

- thoughts about suicide or dying
- attempts to commit suicide
- new or worse depression
- new or worse anxiety
- feeling agitated or restless
- panic attacks

- trouble sleeping (insomnia)
- new or worse irritability
- acting aggressive, being angry, or violent
- acting on dangerous impulses
- an extreme increase in activity and talking (mania)
- other unusual changes in behavior or mood

Do not stop Trokendi XR without first talking to a healthcare provider.

- Stopping Trokendi XR suddenly can cause serious problems.
- Suicidal thoughts or actions can be caused by things other than medicines. If you have suicidal thoughts or actions, your healthcare provider may check for other causes.

How can I watch for early symptoms of suicidal thoughts and actions?

- Pay attention to any changes, especially sudden changes, in mood, behaviors, thoughts, or feelings.
- Keep all follow-up visits with your healthcare provider as scheduled.
- Call your healthcare provider between visits as needed, especially if you are worried about symptoms.

Trokendi XR can harm your unborn baby.

- If you take Trokendi XR during pregnancy, your baby has a higher risk for birth defects including cleft lip and cleft palate. These defects can begin early in pregnancy, even before you know you are pregnant.
- Birth defects may happen even in children born to women who are not taking any medicines and do not have other risk factors.
- There may be other medicines to treat your condition that have a lower chance of birth defects.
- All women of childbearing age should talk to their healthcare providers about using other possible treatments instead of Trokendi XR. If the decision is made to use Trokendi XR, you should use effective birth control (contraception) unless you are planning to become pregnant. You should talk to your doctor about the best kind of birth control to use while you are taking Trokendi XR.
- Tell your healthcare provider right away if you become pregnant while taking Trokendi XR. You and your healthcare provider should decide if you will continue to take Trokendi XR while you are pregnant.
- If you take Trokendi XR during pregnancy, your baby may be smaller than expected at birth. The long-term effects of this are not known. Talk to your healthcare provider if you have questions about this risk during pregnancy.
- Metabolic acidosis may have harmful effects on your baby. Talk to your healthcare provider if Trokendi XR has caused metabolic acidosis during your pregnancy.
- Pregnancy Registry: If you become pregnant while taking Trokendi XR, talk to your healthcare provider about registering with the North American Antiepileptic Drug Pregnancy Registry. You can enroll in this registry by calling 1-888-233-2334. The purpose of this registry is to collect information about the safety of Trokendi XR and other antiepileptic drugs during pregnancy.

Trokendi XR may decrease the density of bones when used over a long period.
Trokendi XR may slow height increase and weight gain in children and adolescents when used over a long period.

What is Trokendi XR?
Trokendi XR is a prescription medicine used:

- to treat certain types of seizures (partial onset seizures and primary generalized tonic-clonic seizures) in people 6 years and older,
- with other medicines to treat certain types of seizures (partial onset seizures, primary generalized tonic-clonic seizures, and seizures associated with Lennox-Gastaut syndrome) in adults and children 6 years and older
- to prevent migraine headaches in adults and adolescents 12 years of age and older.

Before taking Trokendi XR, tell your healthcare provider about all of your medical conditions, including if you:

- have or have had depression, mood problems, or suicidal thoughts or behavior
- have kidney problems, kidney stones, or are getting kidney dialysis
- have a history of metabolic acidosis (too much acid in the blood)
- have liver problems
- have weak, brittle or soft bones (osteomalacia, osteoporosis, osteopenia, or decreased bone density)
- have lung or breathing problems
- have eye problems, especially glaucoma
- have diarrhea
- have a growth problem
- are on a diet high in fat and low in carbohydrates, which is called a ketogenic diet
- are having surgery
- are pregnant or plan to become pregnant
- are breastfeeding. Trokendi XR passes into your breast milk. Breastfed babies may be sleepy or have diarrhea. It is not known if the Trokendi XR that passes into breast milk can cause other serious harm to your baby. Talk to your healthcare provider about the best way to feed your baby if you take Trokendi XR.

Tell your healthcare provider about all the medicines you take, including prescription and over-the-counter medicines, vitamins, and herbal supplements. Especially, tell your healthcare provider if you take:

- Valproic acid (such as DEPAKENE or DEPAKOTE).
- any medicines that impair or decrease your thinking, concentration, or muscle coordination.
- birth control that contains hormones (such as pills, implants, patches, or injections). Trokendi XR may make your birth control less effective. Tell your healthcare provider if your menstrual bleeding changes while you are using birth control and Trokendi XR.

Ask your healthcare provider if you are not sure if your medicine is listed above.
Know the medicines you take. Keep a list of them to show your healthcare provider and pharmacist each time you get a new medicine. Do not start a new medicine without talking with your healthcare provider.

How should I take Trokendi XR?

- Take Trokendi XR exactly as prescribed.
- Your healthcare provider may change your dose. Do notchange your dose without talking to your healthcare provider.
- Take Trokendi XR capsules whole. Do notsprinkle Trokendi XR on food, or break, crush, dissolve, or chew Trokendi XR capsules before swallowing.
- Trokendi XR can be taken before, during, or after a meal. Drink plenty of fluids during the day. This may help prevent kidney stones while taking Trokendi XR.
- If you take too much Trokendi XR, call your healthcare provider right away or go to the nearest emergency room.
- Talk to your health care provider on what you should do if you miss a dose.
- Do not stop taking Trokendi XR without talking to your healthcare provider. Stopping Trokendi XR suddenly may cause serious problems. If you have epilepsy and you stop taking Trokendi XR suddenly, you may have seizures that do not stop. Your healthcare provider will tell you how to stop taking Trokendi XR slowly.
- Your healthcare provider may do blood tests while you take Trokendi XR.

What should I avoid while taking Trokendi XR?

- Do not drink alcohol within 6 hours before or 6 hours after taking Trokendi XR capsules. Trokendi XR and alcohol can cause serious side effects such as severe sleepiness and dizziness and an increase in seizures.
- Do not drive a car or operate heavy machinery until you know how Trokendi XR affects you. Trokendi XR can slow your thinking and motor skills and may affect vision.

What are the possible side effects of Trokendi XR?
Trokendi XR may cause serious side effects, including:
See " What is the most important information I should know about Trokendi XR?"

- Serious skin reactions.Trokendi XR may cause a severe rash with blisters and peeling skin, especially around the mouth, nose, eyes, and genitals (Stevens-Johnson syndrome). Trokendi XR may also cause a rash with blisters and peeling skin over much of the body that may cause death (toxic epidermal necrolysis). Call your healthcare provider right away if you develop a skin rash or blisters.
- High blood ammonia levels.High ammonia in the blood can affect your mental activities, slow your alertness, make you feel tired, or cause vomiting. This has happened when Trokendi XR is taken with a medicine called valproic acid (DEPAKENE and DEPAKOTE).
- Kidney stones.Drink plenty of fluids when taking Trokendi XR to decrease your chances of getting kidney stones.
- Low body temperature.Taking Trokendi XR when you are also taking valproic acid cause a drop in body temperature to less than 95°F, feeling tired, confusion, or coma.
- Effects on thinking and alertness.Trokendi XR may affect how you think, and cause confusion, problems with concentration, attention, memory, or speech. Trokendi XR may cause depression or mood problems, tiredness, and sleepiness.
- Dizziness or loss of muscle coordination.

Call your healthcare provider right away if you have any of the symptoms above.
The most common side effects of Trokendi XR include:

- tingling of the arms and legs (paresthesia)
- not feeling hungry
- nausea
- weight loss
- abnormal vision
- a change in the way foods taste

- nervousness
- speech problems
- dizziness
- slow reactions
- upper respiratory tract infection

- fever
- tiredness
- sleepiness/drowsiness
- difficulty with memory
- diarrhea
- pain in abdomen
- decreased feeling or sensitivity, especially in the skin

Tell your healthcare provider about any side effect that bothers you or that does not go away.
These are not all the possible side effects of Trokendi XR.
Call your doctor for medical advice about side effects. You may report side effects to FDA at 1-800-FDA-1088.
You may also report side effects to Supernus Pharmaceuticals, Inc. at 1-866-398-0833.

How should I store Trokendi XR?

- Store Trokendi XR capsules at room temperature between 59°F to 86°F (15°C to 30°C).
- Keep Trokendi XR in a tightly closed container.
- Keep Trokendi XR dry and away from moisture and light.
- Keep Trokendi XR and all medicines out of the reach of children.

General information about the safe and effective use of Trokendi XR.
Medicines are sometimes prescribed for purposes other than those listed in a Medication Guide. Do not use Trokendi XR for a condition for which it was not prescribed. Do not give Trokendi XR to other people, even if they have the same symptoms that you have. It may harm them.
You can ask your pharmacist or healthcare provider for information about Trokendi XR that is written for health professionals.

What are the ingredients in Trokendi XR?
Active ingredient:topiramate
Inactive ingredients:Sugar spheres, NF; hypromellose (Type 2910), USP; mannitol, USP; docusate sodium, USP; sodium benzoate, NF; ethylcellulose, NF; oleic acid, NF; medium chain triglycerides, NF; polyethylene glycol, NF; polyvinyl alcohol, USP; titanium dioxide, USP; talc, USP; lecithin, NF; xanthan gum, NF; glycerin, USP-NF.
Capsule shells:Gelatin, USP; titanium dioxide, USP; colorants.
Colorants:
FD&C Blue #1 (all strength capsules)
Yellow iron oxide, USP (25 mg and 50 mg capsules)
FD&C red #3 (50 mg, 100 mg, and 200 mg capsules)
FD&C yellow #6 (50 mg, 100 mg, and 200 mg capsules)
Riboflavin, USP (25 mg capsules)
All capsule shells are imprinted with black print that contains shellac, NF, and black iron oxide, NF.
Manufactured by: Catalent Pharma Solutions, Winchester, KY USA 40391
Manufactured for: Supernus Pharmaceuticals, Inc. Rockville, MD USA 20850
© Supernus Pharmaceuticals
RA-TRO-MGV12
For more information, go to www.trokendixr.com or call 1-866-398-0833.

This Medication Guide has been approved by the U.S. Food and Drug Administration

Revised: 3/2025

PRINCIPAL DISPLAY PANEL - 25 mg Capsule Bottle Label

30 Capsules
NDC 17772-101-30

Trokendi XR®
(topiramate) extended-release capsules

Once daily.

Swallow capsule
whole and intact.
Do not open, crush,
chew, or sprinkle
capsule contents on food.

25 mg

ATTENTION PHARMACIST: Dispense
the Accompanying Medication Guide
to Each Patient

Supernus®
Pharmaceuticals
Rx only

PRINCIPAL DISPLAY PANEL - 50 mg Capsule Bottle Label

30 Capsules
NDC 17772-102-30

Trokendi XR®
(topiramate) extended-release capsules

Once daily.

Swallow capsule
whole and intact.
Do not open, crush,
chew, or sprinkle
capsule contents on food.

50 mg

ATTENTION PHARMACIST: Dispense
the Accompanying Medication Guide
to Each Patient

Supernus®
Pharmaceuticals
Rx only

PRINCIPAL DISPLAY PANEL - 100 mg Capsule Bottle Label

30 Capsules
NDC 17772-103-30

Trokendi XR®
(topiramate) extended-release capsules

Once daily.

Swallow capsule
whole and intact.
Do not open, crush,
chew, or sprinkle
capsule contents on food.

100 mg

ATTENTION PHARMACIST: Dispense
the Accompanying Medication Guide
to Each Patient

Supernus®
Pharmaceuticals
Rx only

PRINCIPAL DISPLAY PANEL - 200 mg Capsule Bottle Label

30 Capsules
NDC 17772-104-30

Trokendi XR®
(topiramate) extended-release capsules

Once daily.

Swallow capsule
whole and intact.
Do not open, crush,
chew, or sprinkle
capsule contents on food.

200 mg

ATTENTION PHARMACIST: Dispense
the Accompanying Medication Guide
to Each Patient

Supernus®
Pharmaceuticals
Rx only